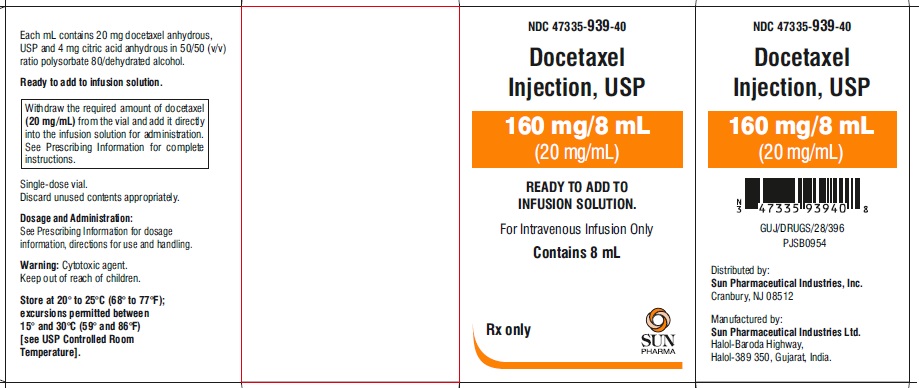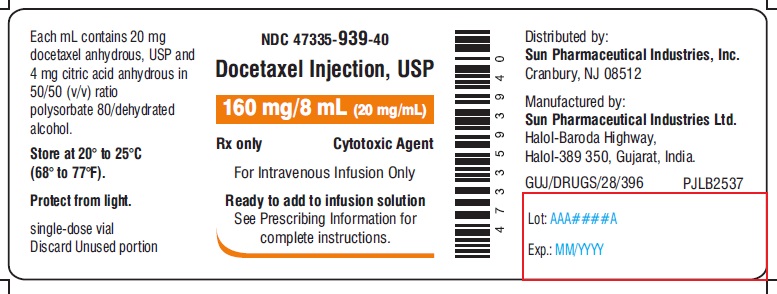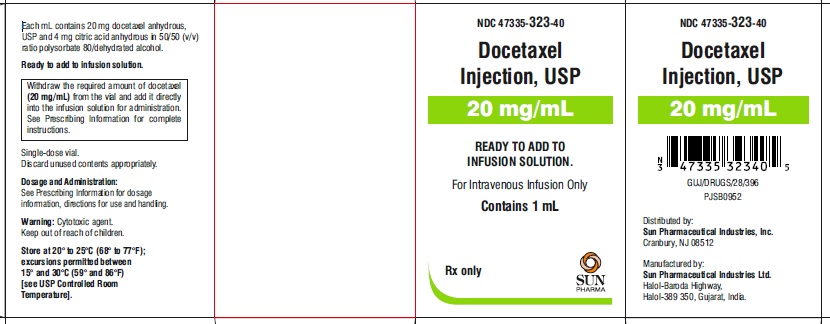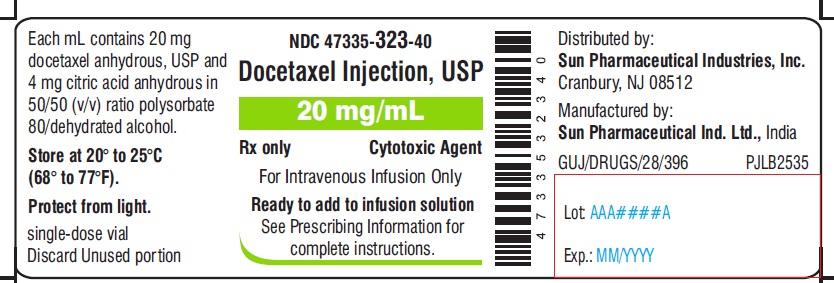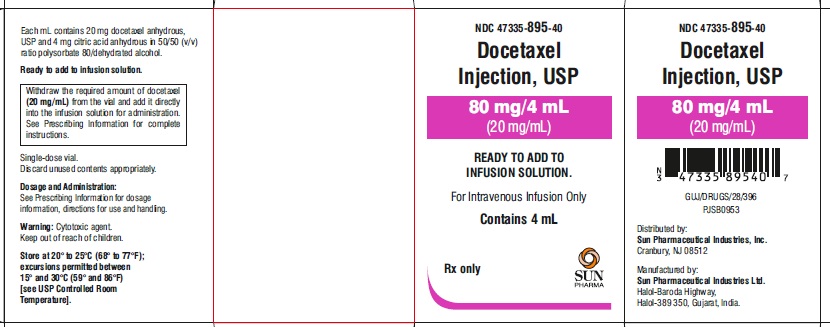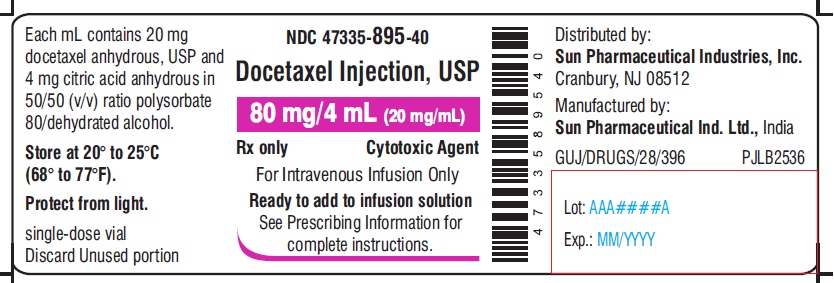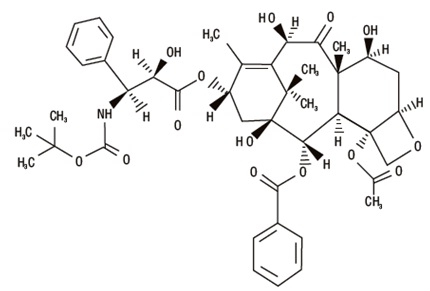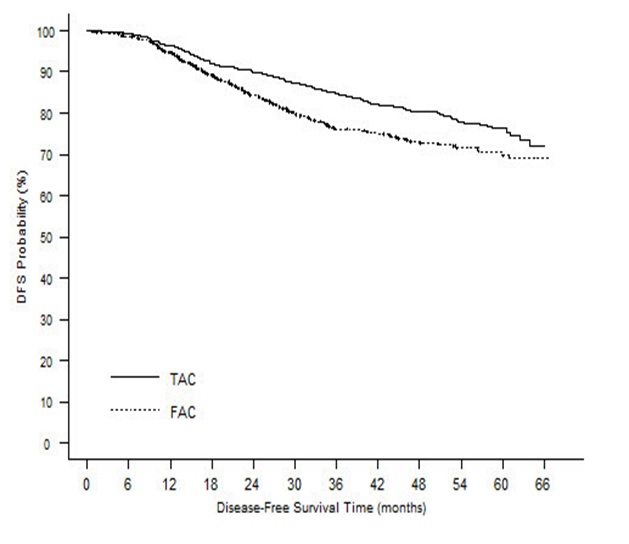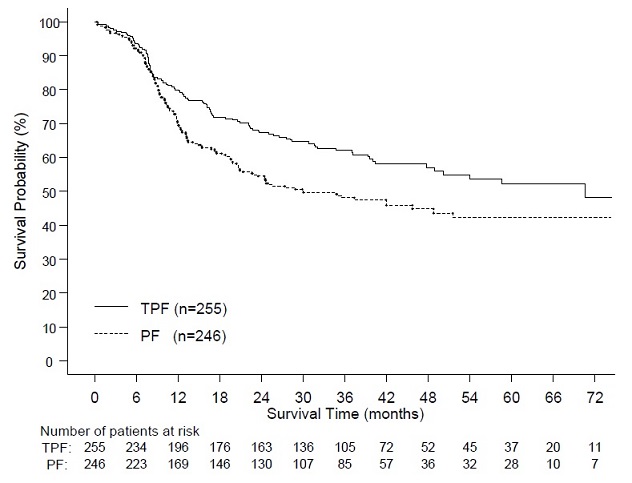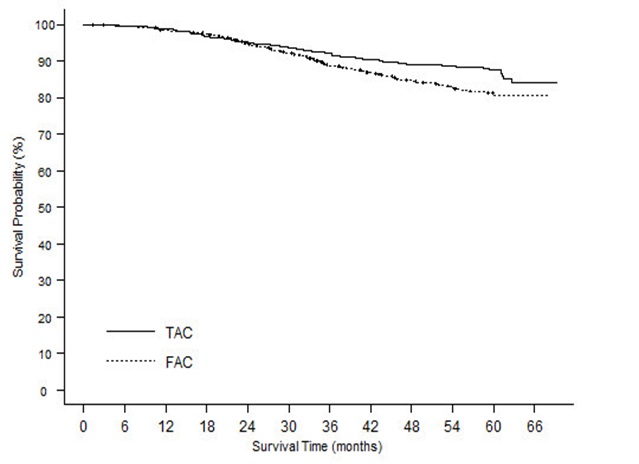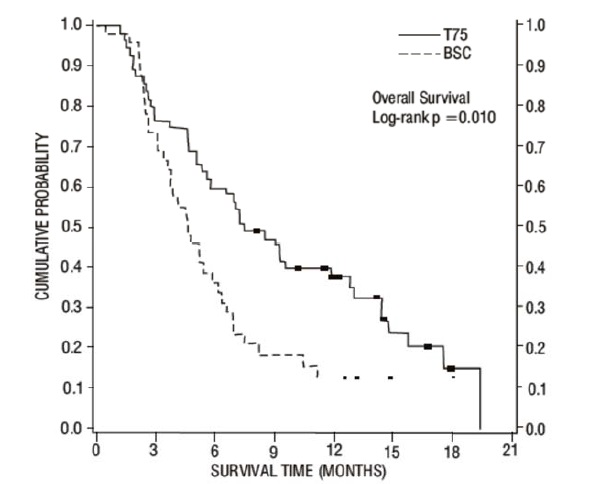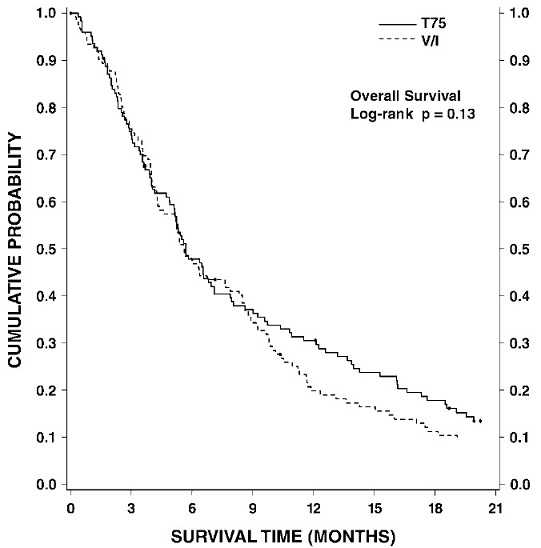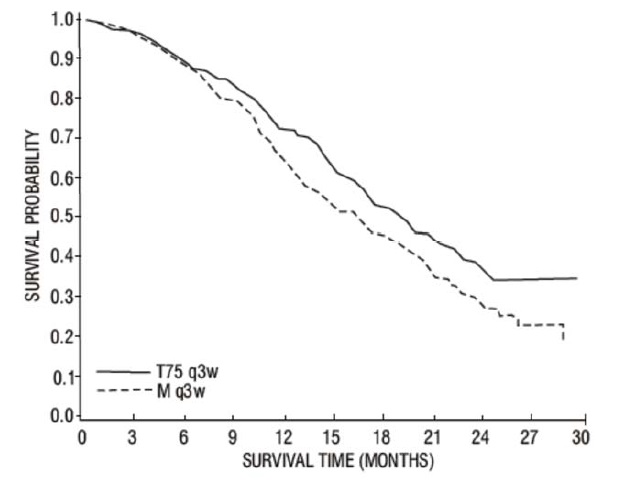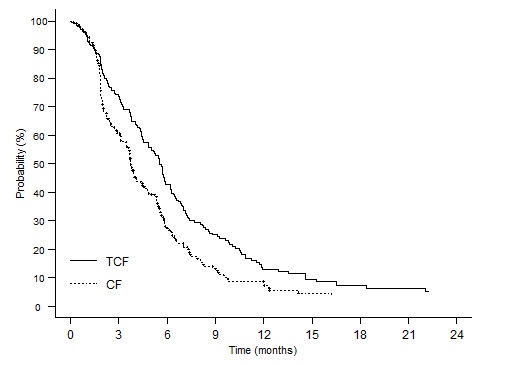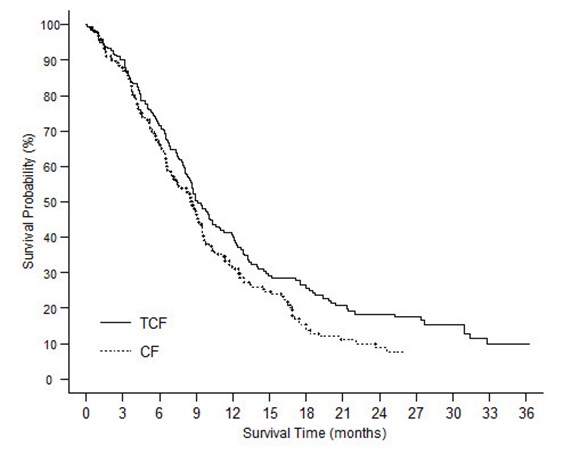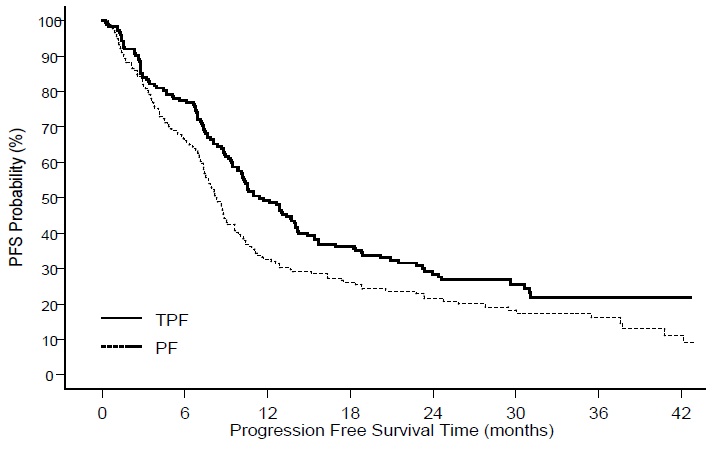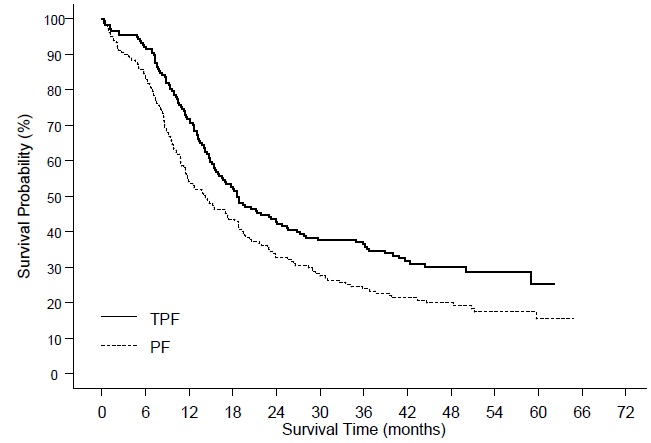 DRUG LABEL: Docetaxel
NDC: 47335-323 | Form: INJECTION, SOLUTION
Manufacturer: Sun Pharmaceutical Industries, Inc.
Category: prescription | Type: Human Prescription Drug Label
Date: 20210204

ACTIVE INGREDIENTS: DOCETAXEL ANHYDROUS 20 mg/1 mL
INACTIVE INGREDIENTS: POLYSORBATE 80 0.54 g/1 mL; ANHYDROUS CITRIC ACID 0.004 g/1 mL; ALCOHOL 0.395 g/1 mL

HIGHLIGHTS OF PRESCRIBING INFORMATION

These highlights do not include all the information needed to use DOCETAXEL INJECTION safely and effectively. See full prescribing information for DOCETAXEL INJECTION.
DOCETAXEL injection, for intravenous use
Initial U.S. Approval: 1996

RECENT MAJOR CHANGES

Warnings and Precautions (5.2, 5.7, 5.8, 5.12) 2/2020

Warnings and Precautions (5.14) 2/2021

WARNING: TOXIC DEATHS, HEPATOTOXICITY, NEUTROPENIA, HYPERSENSITIVITY REACTIONS, and FLUID RETENTION

See full prescribing information for complete boxed warning.
• Treatment-related mortality increases with abnormal liver function, at higher doses, and in patients with NSCLC and prior platinum-based therapy receiving docetaxel at 100 mg/m2 (5.1)
• Avoid use of DOCETAXEL INJECTION if bilirubin > ULN, or if AST and/or ALT > 1.5 x ULN concomitant with alkaline phosphatase > 2.5 x ULN. LFT elevations increase risk of severe or life-threatening complications. Obtain LFTs before each treatment cycle (5.2)
• Do not administer DOCETAXEL INJECTION to patients with neutrophil counts <1,500 cells/mm3. Obtain frequent blood counts to monitor for neutropenia (4, 5.3)
• Severe hypersensitivity, including fatal anaphylaxis, has been reported in patients who received dexamethasone premedication. Severe reactions require immediate discontinuation of DOCETAXEL INJECTION and administration of appropriate therapy (5.5)
• Contraindicated if history of severe hypersensitivity reactions to docetaxel or to drugs formulated with polysorbate 80 (4)
• Severe fluid retention may occur despite dexamethasone (5.6)

1 INDICATIONS AND USAGE

DOCETAXEL INJECTION is a microtubule inhibitor indicated for:

- Breast Cancer (BC): single agent for locally advanced or metastatic BC after chemotherapy failure; and with doxorubicin and cyclophosphamide as adjuvant treatment of operable node-positive BC (1.1)
- Non-small Cell Lung Cancer (NSCLC): single agent for locally advanced or metastatic NSCLC after platinum therapy failure; and with cisplatin for unresectable, locally advanced or metastatic untreated NSCLC (1.2)
- Castration-Resistant Prostate Cancer (CRPC): with prednisone in metastatic castration-resistant prostate cancer (1.3)
- Gastric Adenocarcinoma (GC): with cisplatin and fluorouracil for untreated, advanced GC, including the gastroesophageal junction (1.4)
- Squamous Cell Carcinoma of the Head and Neck (SCCHN): with cisplatin and fluorouracil for induction treatment of locally advanced SCCHN (1.5)

2 DOSAGE AND ADMINISTRATION

Administer in a facility equipped to manage possible complications (e.g., anaphylaxis). Administer intravenously (IV) over 1 hour every 3 weeks. PVC equipment is not recommended. Use only a 21 gauge needle to withdraw DOCETAXEL INJECTION from the vial.

- BC locally advanced or metastatic: 60 mg/m2 to 100 mg/m^2 single agent (2.1)
- BC adjuvant: 75 mg/m^2 administered 1 hour after doxorubicin 50 mg/m^2 and cyclophosphamide 500 mg/m^2 every 3 weeks for 6 cycles (2.1)
- NSCLC: after platinum therapy failure: 75 mg/m^2 single agent (2.2)
- NSCLC: chemotherapy naive: 75 mg/m^2 followed by cisplatin 75 mg/m^2 (2.2)
- HRPC: 75 mg/m^2 with 5 mg prednisone twice a day continuously (2.3)
- GC: 75 mg/m^2 followed by cisplatin 75 mg/m^2 (both on day 1 only) followed by fluorouracil 750 mg/m^2 per day as a 24-hour IV (days 1 to 5), starting at end of cisplatin infusion (2.4)
- SCCHN: 75 mg/m^2 followed by cisplatin 75 mg/m^2 IV (day 1), followed by fluorouracil 750 mg/m^2 per day as a 24-hour IV (days 1 to 5), starting at end of cisplatin infusion; for 4 cycles (2.5)
- SCCHN: 75 mg/m^2 followed by cisplatin 100 mg/m^2 IV (day 1), followed by fluorouracil 1,000 mg/m^2 per day as a 24-hour IV (days 1 to 4); for 3 cycles (2.5)

For all patients:

- Premedicate with oral corticosteroids (2.6)
- Adjust dose as needed (2.7)

3 DOSAGE FORMS AND STRENGTHS

- One-vial DOCETAXEL INJECTION: Single-dose vials 20 mg/mL, 80 mg/4 mL and 160 mg/8 mL (3)

4 CONTRAINDICATIONS

- Hypersensitivity to docetaxel or polysorbate 80 (4)
- Neutrophil counts of < 1,500 cells/mm^3 (4)

5 WARNINGS AND PRECAUTIONS

- Second primary malignancies: In patients treated with DOCETAXEL INJECTION-containing regimens, monitor for delayed AML, MDS, NHL, and renal cancer. (5.7)
- Cutaneous reactions: Reactions including erythema of the extremities with edema followed by desquamation may occur. Severe cutaneous adverse reactions have been reported. Severe skin toxicity may require dose adjustment or permanent treatment discontinuation. (5.8)
- Neurologic reactions: Reactions including paresthesia, dysesthesia, and pain may occur. Severe neurosensory symptoms require dose adjustment or discontinuation if persistent. (5.9)
- Eye disorders: Cystoid macular edema (CME) has been reported and requires treatment discontinuation. (5.10)
- Asthenia: Severe asthenia may occur and may require treatment discontinuation. (5.11)
- Embryo-fetal toxicity: Can cause fetal harm. Advise patients of the potential risk to a fetus and to use effective contraception. (5.12, 8.1, 8.3)
- Alcohol content: The alcohol content in a dose of DOCETAXEL INJECTION may affect the central nervous system. This may include impairment of a patient's ability to drive or use machines immediately after infusion. (5.13)
- Tumor lysis syndrome: Tumor lysis syndrome has been reported. Patients at risk should be well hydrated and closely monitored during treatment. (5.14)

6 ADVERSE REACTIONS

Most common adverse reactions across all docetaxel indications are infections, neutropenia, anemia, febrile neutropenia, hypersensitivity, thrombocytopenia, neuropathy, dysgeusia, dyspnea, constipation, anorexia, nail disorders, fluid retention, asthenia, pain, nausea, diarrhea, vomiting, mucositis, alopecia, skin reactions, and myalgia. (6)

To report SUSPECTED ADVERSE REACTIONS, contact Sun Pharmaceutical Industries, Inc. at 1-800-818-4555 or FDA at 1-800-FDA-1088 or www.fda.gov/medwatch

7 DRUG INTERACTIONS

- Cytochrome P450 3A4 inducers, inhibitors, or substrates: May alter docetaxel metabolism. (7)

8 USE IN SPECIFIC POPULATIONS

- Lactation: Advise women not to breastfeed. (8.2)
- Females and Males of Reproductive Potential: Verify pregnancy status of females prior to initiation of DOCETAXEL INJECTION. (8.3)

FULL PRESCRIBING INFORMATION

WARNING: TOXIC DEATHS, HEPATOTOXICITY, NEUTROPENIA, HYPERSENSITIVITY REACTIONS, and FLUID RETENTION

Treatment-related mortality associated with docetaxel is increased in patients with abnormal liver function, in patients receiving higher doses, and in patients with non-small cell lung carcinoma and a history of prior treatment with platinum-based chemotherapy who receive DOCETAXEL INJECTION as a single agent at a dose of 100 mg/m^2

[see Warnings and Precautions (5.1)].

Avoid the use of DOCETAXEL INJECTION in patients with bilirubin > upper limit of normal (ULN), or to patients with AST and/or ALT >1.5 x ULN concomitant with alkaline phosphatase >2.5 x ULN. Patients with elevations of bilirubin or abnormalities of transaminase concurrent with alkaline phosphatase are at increased risk for the development of severe neutropenia, febrile neutropenia, infections, severe thrombocytopenia, severe stomatitis, severe skin toxicity, and toxic death. Patients with isolated elevations of transaminase >1.5 x ULN also had a higher rate of febrile neutropenia. Measure bilirubin, AST or ALT, and alkaline phosphatase prior to each cycle of DOCETAXEL INJECTION [see Warnings and Precautions (5.2)].

Do not administer DOCETAXEL INJECTION to patients with neutrophil counts of <1,500 cells/mm^3. Monitor blood cell counts frequently as neutropenia may be severe and result in infection [see Warnings and Precautions (5.3)].

Do not administer DOCETAXEL INJECTION to patients who have a history of severe hypersensitivity reactions to docetaxel or to other drugs formulated with polysorbate 80 [see Contraindications (4)]. Severe hypersensitivity reactions have been reported in patients despite dexamethasone premedication. Hypersensitivity reactions require immediate discontinuation of the DOCETAXEL INJECTION infusion and administration of appropriate therapy [see Warnings and Precautions (5.5)].

Severe fluid retention occurred in 6.5% (6/92) of patients despite use of dexamethasone premedication. It was characterized by one or more of the following events: poorly tolerated peripheral edema, generalized edema, pleural effusion requiring urgent drainage, dyspnea at rest, cardiac tamponade, or pronounced abdominal distention (due to ascites) [see Warnings and Precautions (5.6)].

1 INDICATIONS AND USAGE

1.1 Breast Cancer

DOCETAXEL INJECTION is indicated for the treatment of patients with locally advanced or metastatic breast cancer after failure of prior chemotherapy.

DOCETAXEL INJECTION in combination with doxorubicin and cyclophosphamide is indicated for the adjuvant treatment of patients with operable node-positive breast cancer.

1.2 Non-small Cell Lung Cancer

DOCETAXEL INJECTION as a single agent is indicated for the treatment of patients with locally advanced or metastatic non-small cell lung cancer after failure of prior platinum-based chemotherapy.

DOCETAXEL INJECTION in combination with cisplatin is indicated for the treatment of patients with unresectable, locally advanced or metastatic non-small cell lung cancer who have not previously received chemotherapy for this condition.

1.3 Prostate Cancer

DOCETAXEL INJECTION in combination with prednisone is indicated for the treatment of patients with metastatic castration-resistant prostate cancer.

1.4 Gastric Adenocarcinoma

DOCETAXEL INJECTION in combination with cisplatin and fluorouracil is indicated for the treatment of patients with advanced gastric adenocarcinoma, including adenocarcinoma of the gastroesophageal junction, who have not received prior chemotherapy for advanced disease.

1.5 Head and Neck Cancer

DOCETAXEL INJECTION in combination with cisplatin and fluorouracil is indicated for the induction treatment of patients with locally advanced squamous cell carcinoma of the head and neck (SCCHN).

2 DOSAGE AND ADMINISTRATION

For all indications, toxicities may warrant dosage adjustments [see Dosage and Administration (2.7)].

Administer in a facility equipped to manage possible complications (e.g., anaphylaxis).

2.1 Breast Cancer

- For locally advanced or metastatic breast cancer after failure of prior chemotherapy, the recommended dose of DOCETAXEL INJECTION is 60 mg/m^2 to 100 mg/m^2 administered intravenously over 1 hour every 3 weeks.
- For the adjuvant treatment of operable node-positive breast cancer, the recommended DOCETAXEL INJECTION dose is 75 mg/m2 administered 1 hour after doxorubicin 50 mg/m2 and cyclophosphamide 500 mg/m^2 every 3 weeks for 6 courses. Prophylactic G-CSF may be used to mitigate the risk of hematological toxicities [see Dosage and Administration (2.7)].

2.2 Non-small Cell Lung Cancer

- For treatment after failure of prior platinum-based chemotherapy, docetaxel was evaluated as monotherapy, and the recommended dose is 75 mg/m^2 administered intravenously over 1 hour every 3 weeks. A dose of 100 mg/m^2 in patients previously treated with chemotherapy was associated with increased hematologic toxicity, infection, and treatment-related mortality in randomized controlled trials [see Boxed Warning, Dosage and Administration (2.7), Warnings and Precautions (5), Clinical Studies (14)].
- For chemotherapy-naive patients, docetaxel was evaluated in combination with cisplatin. The recommended dose of DOCETAXEL INJECTION is 75 mg/m^2 administered intravenously over 1 hour immediately followed by cisplatin 75 mg/m^2 over 30 to 60 minutes every 3 weeks [see Dosage and Administration (2.7)].

2.3 Prostate Cancer

- For metastatic castration-resistant prostate cancer, the recommended dose of DOCETAXEL INJECTION is 75 mg/m^2 every 3 weeks as a 1 hour intravenous infusion. Prednisone 5 mg orally twice daily is administered continuously [see Dosage and Administration (2.7)].

2.4 Gastric Adenocarcinoma

- For gastric adenocarcinoma, the recommended dose of DOCETAXEL INJECTION is 75 mg/m^2 as a 1 hour intravenous infusion, followed by cisplatin 75 mg/m^2, as a 1 to 3 hour intravenous infusion (both on day 1 only), followed by fluorouracil 750 mg/m^2 per day given as a 24-hour continuous intravenous infusion for 5 days, starting at the end of the cisplatin infusion. Treatment is repeated every three weeks. Patients must receive premedication with antiemetics and appropriate hydration for cisplatin administration [see Dosage and Administration (2.7)].

2.5 Head and Neck Cancer

Patients must receive premedication with antiemetics, and appropriate hydration (prior to and after cisplatin administration). Prophylaxis for neutropenic infections should be administered. All patients treated on the docetaxel containing arms of the TAX323 and TAX324 studies received prophylactic antibiotics.

- Induction Chemotherapy Followed by Radiotherapy (TAX323)

For the induction treatment of locally advanced inoperable SCCHN, the recommended dose of DOCETAXEL INJECTION is 75 mg/m^2 as a 1 hour intravenous infusion followed by cisplatin 75 mg/m^2 intravenously over 1 hour, on day one, followed by fluorouracil as a continuous intravenous infusion at 750 mg/m^2 per day for five days. This regimen is administered every 3 weeks for 4 cycles. Following chemotherapy, patients should receive radiotherapy [see Dosage and Administration (2.7)].

- Induction Chemotherapy Followed by Chemoradiotherapy (TAX324)

For the induction treatment of patients with locally advanced (unresectable, low surgical cure, or organ preservation) SCCHN, the recommended dose of DOCETAXEL INJECTION is 75 mg/m^2 as a 1 hour intravenous infusion on day 1, followed by cisplatin 100 mg/m^2 administered as a 30-minute to 3 hour infusion, followed by fluorouracil 1,000 mg/m^2/day as a continuous infusion from day 1 to day 4. This regimen is administered every 3 weeks for 3 cycles. Following chemotherapy, patients should receive chemoradiotherapy [see Dosage and Administration (2.7)].

2.6 Premedication Regimen

All patients should be premedicated with oral corticosteroids (see below for prostate cancer) such as dexamethasone 16 mg per day (e.g., 8 mg twice daily) for 3 days starting 1 day prior to DOCETAXEL INJECTION administration in order to reduce the incidence and severity of fluid retention as well as the severity of hypersensitivity reactions [see Boxed Warning, Warnings and Precautions (5.5)].

For metastatic castration-resistant prostate cancer, given the concurrent use of prednisone, the recommended premedication regimen is oral dexamethasone 8 mg at 12 hours, 3 hours, and 1 hour before the DOCETAXEL INJECTION infusion [see Warnings and Precautions (5.5)].

2.7 Dosage Adjustments during Treatment

Breast Cancer

Patients who are dosed initially at 100 mg/m^2 and who experience either febrile neutropenia, neutrophils <500 cells/mm^3 for more than 1 week, or severe or cumulative cutaneous reactions during DOCETAXEL INJECTION therapy should have the dosage adjusted from 100 mg/m^2 to 75 mg/m^2 . If the patient continues to experience these reactions, the dosage should either be decreased from 75 mg/m^2 to 55 mg/m^2 or the treatment should be discontinued. Conversely, patients who are dosed initially at 60 mg/m^2 and who do not experience febrile neutropenia, neutrophils <500 cells/mm^3 for more than 1 week, severe or cumulative cutaneous reactions, or severe peripheral neuropathy during DOCETAXEL INJECTION therapy may tolerate higher doses. Patients who develop ≥grade 3 peripheral neuropathy should have DOCETAXEL INJECTION treatment discontinued entirely.
Combination Therapy with DOCETAXEL INJECTION in the Adjuvant Treatment of Breast Cancer

DOCETAXEL INJECTION in combination with doxorubicin and cyclophosphamide should be administered when the neutrophil count is ≥1,500 cells/mm^3. Patients who experience febrile neutropenia should receive G-CSF in all subsequent cycles. Patients who continue to experience this reaction should remain on G-CSF and have their DOCETAXEL INJECTION dose reduced to 60 mg/m². Patients who experience grade 3 or 4 stomatitis should have their DOCETAXEL INJECTION dose decreased to 60 mg/m². Patients who experience severe or cumulative cutaneous reactions or moderate neurosensory signs and/or symptoms during DOCETAXEL INJECTION therapy should have their dosage of DOCETAXEL INJECTION reduced from 75 mg/m² to 60 mg/m². If the patient continues to experience these reactions at 60 mg/m², treatment should be discontinued.
Non-small Cell Lung Cancer

Monotherapy with DOCETAXEL INJECTION for NSCLC treatment after failure of prior platinum-based chemotherapy

Patients who are dosed initially at 75 mg/m^2 and who experience either febrile neutropenia, neutrophils <500 cells/mm^3 for more than one week, severe or cumulative cutaneous reactions, or other grade 3/4 non-hematological toxicities during DOCETAXEL INJECTION treatment should have treatment withheld until resolution of the toxicity and then resumed at 55 mg/m^2 . Patients who develop ≥grade 3 peripheral neuropathy should have DOCETAXEL INJECTION treatment discontinued entirely.
Combination therapy with DOCETAXEL INJECTION for chemotherapy-naive NSCLC

For patients who are dosed initially at DOCETAXEL INJECTION 75 mg/m^2 in combination with cisplatin, and whose nadir of platelet count during the previous course of therapy is <25,000 cells/mm^3, in patients who experience febrile neutropenia, and in patients with serious non-hematologic toxicities, the DOCETAXEL INJECTION dosage in subsequent cycles should be reduced to 65 mg/m^2. In patients who require a further dose reduction, a dose of 50 mg/m^2 is recommended. For cisplatin dosage adjustments, see manufacturers’ prescribing information.
Prostate Cancer

Combination therapy with DOCETAXEL INJECTION for metastatic castration-resistant prostate cancer

DOCETAXEL INJECTION should be administered when the neutrophil count is ≥ 1,500 cells/mm^3. Patients who experience either febrile neutropenia, neutrophils <500 cells/mm^3 for more than one week, severe or cumulative cutaneous reactions or moderate neurosensory signs and/or symptoms during DOCETAXEL INJECTION therapy should have the dosage of DOCETAXEL INJECTION reduced from 75 mg/m^2 to 60 mg/m^2. If the patient continues to experience these reactions at 60 mg/m^2, the treatment should be discontinued.
Gastric or Head and Neck Cancer

DOCETAXEL INJECTION in combination with cisplatin and fluorouracil in gastric cancer or head and neck cancer

Patients treated with DOCETAXEL INJECTION in combination with cisplatin and fluorouracil must receive antiemetics and appropriate hydration according to current institutional guidelines. In both studies, G-CSF was recommended during the second and/or subsequent cycles in case of febrile neutropenia, or documented infection with neutropenia, or neutropenia lasting more than 7 days. If an episode of febrile neutropenia, prolonged neutropenia or neutropenic infection occurs despite G-CSF use, the DOCETAXEL INJECTION dose should be reduced from 75 mg/m^2 to 60 mg/m^2. If subsequent episodes of complicated neutropenia occur the DOCETAXEL INJECTION dose should be reduced from 60 mg/m^2 to 45 mg/m^2. In case of grade 4 thrombocytopenia the DOCETAXEL INJECTION dose should be reduced from 75 mg/m^2 to 60 mg/m^2. Do not retreat patients with subsequent cycles of DOCETAXEL INJECTION until neutrophils recover to a level >1,500 cells/mm^3 [see Contraindications (4)]. Avoid retreating patients until platelets recover to a level >100,000 cells/mm^3. Discontinue treatment if these toxicities persist [see Warnings and Precautions (5.3)].
Recommended dose modifications for toxicities in patients treated with DOCETAXEL INJECTION in combination with cisplatin and fluorouracil are shown in Table 1.
Table 1 - Recommended Dose Modifications for Toxicities in Patients Treated with DOCETAXEL INJECTION in Combination with Cisplatin and Fluorouracil

Toxicity | Dosage adjustment
Diarrhea grade 3 | First episode: reduce fluorouracil dose by 20%. Second episode: then reduce DOCETAXEL INJECTION dose by 20%.
Diarrhea grade 4 | First episode: reduce DOCETAXEL INJECTION and fluorouracil doses by 20%. Second episode: discontinue treatment.
Stomatitis/mucositis grade 3 |  | First episode: reduce fluorouracil dose by 20%. Second episode: stop fluorouracil only, at all subsequent cycles. Third episode: reduce DOCETAXEL INJECTION dose by 20%.
Stomatitis/mucositis grade 4 |  | First episode: stop fluorouracil only, at all subsequent cycles. Second episode: reduce DOCETAXEL INJECTION dose by 20%.

Liver dysfunction:

In case of AST/ALT >2.5 to ≤5 x ULN and AP ≤2.5 x ULN, or AST/ALT >1.5 to ≤5 x ULN and AP >2.5 to ≤5 x ULN, DOCETAXEL INJECTION should be reduced by 20%.
In case of AST/ALT >5 x ULN and/or AP >5 x ULN DOCETAXEL INJECTION should be stopped.
The dose modifications for cisplatin and fluorouracil in the gastric cancer study are provided below.
Cisplatin dose modifications and delays

Peripheral neuropathy: A neurological examination should be performed before entry into the study, and then at least every 2 cycles and at the end of treatment. In the case of neurological signs or symptoms, more frequent examinations should be performed and the following dose modifications can be made according to NCI-CTCAE grade:

- Grade 2: Reduce cisplatin dose by 20%.
- Grade 3: Discontinue treatment.

Ototoxicity: In the case of grade 3 toxicity, discontinue treatment.
Nephrotoxicity: In the event of a rise in serum creatinine ≥grade 2 (>1.5 x normal value) despite adequate rehydration, CrCl should be determined before each subsequent cycle and the following dose reductions should be considered (see Table 2).
For other cisplatin dosage adjustments, also refer to the manufacturers’ prescribing information.
Table 2 – Dose Reductions for Evaluation of Creatinine Clearance

Creatinine clearance result before next cycle | Cisplatin dose next cycle
CrCl ≥60 mL/min | Full dose of cisplatin was given. CrCl was to be repeated before each treatment cycle.
CrCl between 40 and 59 mL/min | Dose of cisplatin was reduced by 50% at subsequent cycle. If CrCl was >60 mL/min at end of cycle, full cisplatin dose was reinstituted at the next cycle. If no recovery was observed, then cisplatin was omitted from the next treatment cycle.
CrCl <40 mL/min | Dose of cisplatin was omitted in that treatment cycle only. If CrCl was still <40 mL/min at the end of cycle, cisplatin was discontinued. If CrCl was >40 and <60 mL/min at end of cycle, a 50% cisplatin dose was given at the next cycle. If CrCl was >60 mL/min at end of cycle, full cisplatin dose was given at next cycle.

CrCl = Creatinine clearance
Fluorouracil dose modifications and treatment delays

For diarrhea and stomatitis, see Table 1.
In the event of grade 2 or greater plantar-palmar toxicity, fluorouracil should be stopped until recovery. The fluorouracil dosage should be reduced by 20%.
For other greater than grade 3 toxicities, except alopecia and anemia, chemotherapy should be delayed (for a maximum of 2 weeks from the planned date of infusion) until resolution to grade ≤1 and then recommenced, if medically appropriate.
For other fluorouracil dosage adjustments, also refer to the manufacturers’ prescribing information.
Combination Therapy with Strong CYP3A4 Inhibitors

Avoid using concomitant strong CYP3A4 inhibitors (e.g., ketoconazole, itraconazole, clarithromycin, atazanavir, indinavir, nefazodone, nelfinavir, ritonavir, saquinavir, telithromycin and voriconazole). There are no clinical data with a dose adjustment in patients receiving strong CYP3A4 inhibitors. Based on extrapolation from a pharmacokinetic study with ketoconazole in 7 patients, consider a 50% docetaxel dose reduction if patients require coadministration of a strong CYP3A4 inhibitor [see Drug Interactions (7), Clinical Pharmacology (12.3)].

2.8 Administration Precautions

DOCETAXEL INJECTION is a cytotoxic anticancer drug and, as with other potentially toxic compounds, caution should be exercised when handling and preparing DOCETAXEL INJECTION solutions. The use of gloves is recommended [see How Supplied/Storage and Handling (16.3)].

If DOCETAXEL INJECTION, initial diluted solution, or final dilution for infusion should come into contact with the skin, immediately and thoroughly wash with soap and water. If DOCETAXEL INJECTION, initial diluted solution, or final dilution for infusion should come into contact with mucosa, immediately and thoroughly wash with water.

Contact of the DOCETAXEL INJECTION with plasticized PVC equipment or devices used to prepare solutions for infusion is not recommended. In order to minimize patient exposure to the plasticizer DEHP (di-2-ethylhexyl phthalate), which may be leached from PVC infusion bags or sets, the final DOCETAXEL INJECTION dilution for infusion should be stored in bottles (glass, polypropylene) or plastic bags (polypropylene, polyolefin) and administered through polyethylene-lined administration sets.

One-vial DOCETAXEL INJECTION

DOCETAXEL INJECTION requires NO prior dilution with a diluent and is ready to add to the infusion solution. Please follow the preparation instructions provided below.

2.9 Preparation and Administration

DO NOT use the two-vial formulation (Injection and diluent) with the one-vial formulation.
One-vial DOCETAXEL INJECTION
DOCETAXEL INJECTION (20 mg/mL) requires NO prior dilution with a diluent and is ready to add to the infusion solution. Use only a 21 gauge needle to withdraw DOCETAXEL INJECTION from the vial because larger bore needles (e.g., 18 and 19 gauge) may result in stopper coring and rubber particulates.

1. DOCETAXEL INJECTION vials should be store at 20° to 25°C (68° to 77°F); excursions permitted between 15° and 30°C (59° and 86°F) [see How Supplied/Storage and Handling (16.2)].
2. Using only a 21 gauge needle, aseptically withdraw the required amount of DOCETAXEL INJECTION (20 mg docetaxel/mL) with a calibrated syringe and inject via a single injection (one shot) into a 250 mL infusion bag or bottle of either 0.9% Sodium Chloride solution or 5% Dextrose solution to produce a final concentration of 0.3 mg/mL to 0.74 mg/mL. If a dose greater than 200 mg of DOCETAXEL INJECTION is required, use a larger volume of the infusion vehicle so that a concentration of 0.74 mg/mL DOCETAXEL INJECTION is not exceeded.
3. Thoroughly mix the infusion by gentle manual rotation.
4. As with all parenteral products, DOCETAXEL INJECTION should be inspected visually for particulate matter or discoloration prior to administration whenever the solution and container permit. If the DOCETAXEL INJECTION dilution for intravenous infusion is not clear or appears to have precipitation, it should be discarded.
5. DOCETAXEL INJECTION infusion solution is supersaturated, therefore may crystallize over time. If crystals appear, the solution must no longer be used and shall be discarded. The DOCETAXEL INJECTION dilution for infusion should be administered intravenously as a 1-hour infusion under ambient room temperature (below 25°C) and lighting conditions.

2.10 Stability

DOCETAXEL INJECTION final dilution for infusion, if stored between 2°C and 25°C (36°F and 77°F) is stable for 6 hours. DOCETAXEL INJECTION final dilution for infusion (in either 0.9% Sodium Chloride solution or 5% Dextrose solution) should be used within 6 hours (including the 1 hour intravenous administration).

In addition, physical and chemical in-use stability of the infusion solution prepared as recommended has been demonstrated in non-PVC bags up to 48 hours when stored between 2°C and 8°C (36°F and 46°F).

3 DOSAGE FORMS AND STRENGTHS

One-vial DOCETAXEL INJECTION
DOCETAXEL INJECTION 20 mg/mL

DOCETAXEL INJECTION 20 mg/1 mL single-dose vial: 20 mg docetaxel in 1 mL in 50/50 (v/v) ratio polysorbate 80/dehydrated alcohol.

DOCETAXEL INJECTION 80 mg/4 mL

DOCETAXEL INJECTION 80 mg/4 mL single-dose vial: 80 mg docetaxel in 4 mL 50/50 (v/v) ratio polysorbate 80/dehydrated alcohol.

DOCETAXEL INJECTION 160 mg/8 mL

DOCETAXEL INJECTION 160 mg/8 mL single-dose vial: 160 mg docetaxel in 8 mL 50/50 (v/v) ratio polysorbate 80/dehydrated alcohol.

4 CONTRAINDICATIONS

DOCETAXEL INJECTION is contraindicated in patients with:

- neutrophil counts of < 1,500 cells/mm3 [see Warnings and Precautions (5.3)].
- a history of severe hypersensitivity reactions to docetaxel or to other drugs formulated with polysorbate 80. Severe reactions, including anaphylaxis, have occurred [see Warnings and Precautions (5.5)].

5 WARNINGS AND PRECAUTIONS

5.1 Toxic Deaths

Breast Cancer

Docetaxel administered at 100 mg/m^2 was associated with deaths considered possibly or probably related to treatment in 2% (19/965) of metastatic breast cancer patients, both previously treated and untreated, with normal baseline liver function and in 11.5% (7/61) of patients with various tumor types who had abnormal baseline liver function (AST and/or ALT >1.5 times ULN together with AP >2.5 times ULN). Among patients dosed at 60 mg/m^2, mortality related to treatment occurred in 0.6% (3/481) of patients with normal liver function, and in 3 of 7 patients with abnormal liver function. Approximately half of these deaths occurred during the first cycle. Sepsis accounted for the majority of the deaths.

Non-small Cell Lung Cancer

Docetaxel administered at a dose of 100 mg/m^2 in patients with locally advanced or metastatic non-small cell lung cancer who had a history of prior platinum-based chemotherapy was associated with increased treatment-related mortality (14% and 5% in two randomized, controlled studies). There were 2.8% treatment-related deaths among the 176 patients treated at the 75 mg/m^2 dose in the randomized trials. Among patients who experienced treatment-related mortality at the 75 mg/m^2 dose level, 3 of 5 patients had an ECOG PS of 2 at study entry [see Dosage and Administration (2.2), Clinical Studies (14)].

5.2 Hepatic Impairment

Patients with elevations of bilirubin or abnormalities of transaminase concurrent with alkaline phosphatase are at increased risk for the development of severe neutropenia, febrile neutropenia, infections, severe thrombocytopenia, severe stomatitis, severe skin toxicity, and toxic death.

Avoid DOCETAXEL INJECTION in patients with bilirubin > upper limit of normal (ULN), or to patients with AST and/or ALT >1.5 × ULN concomitant with alkaline phosphatase >2.5 × ULN [see Warnings and Precautions (5.1)].

For patients with isolated elevations of transaminase >1.5 × ULN, consider DOCETAXEL INJECTION dose modifications [see Dosage and Administration (2.7)].

Measure bilirubin, AST or ALT, and alkaline phosphatase prior to each cycle of DOCETAXEL INJECTION therapy.

5.3 Hematologic Effects

Perform frequent peripheral blood cell counts on all patients receiving DOCETAXEL INJECTION. Do not retreat patients with subsequent cycles of DOCETAXEL INJECTION until neutrophils recover to a level > 1,500 cells/mm^3 [see Contraindications (4)]. Avoid retreating patients until platelets recover to a level > 100,000 cells/mm^3.

A 25% reduction in the dose of DOCETAXEL INJECTION is recommended during subsequent cycles following severe neutropenia (<500 cells/mm^3) lasting 7 days or more, febrile neutropenia, or a grade 4 infection in a DOCETAXEL INJECTION cycle [see Dosage and Administration (2.7)].

Neutropenia (<2000 neutrophils/mm^3) occurs in virtually all patients given 60 mg/m^2 to 100 mg/m^2 of docetaxel and grade 4 neutropenia (<500 cells/mm^3) occurs in 85% of patients given 100 mg/m^2 and 75% of patients given 60 mg/m^2. Frequent monitoring of blood counts is, therefore, essential so that dose can be adjusted. DOCETAXEL INJECTION should not be administered to patients with neutrophils <1,500 cells/mm^3.

Febrile neutropenia occurred in about 12% of patients given 100 mg/m^2 but was very uncommon in patients given 60 mg/m^2. Hematologic responses, febrile reactions and infections, and rates of septic death for different regimens are dose related [see Adverse Reactions (6.1), Clinical Studies (14)].

Three breast cancer patients with severe liver impairment (bilirubin >1.7 times ULN) developed fatal gastrointestinal bleeding associated with severe drug-induced thrombocytopenia. In gastric cancer patients treated with docetaxel in combination with cisplatin and fluorouracil (TCF), febrile neutropenia and/or neutropenic infection occurred in 12% of patients receiving G-CSF compared to 28% who did not. Patients receiving TCF should be closely monitored during the first and subsequent cycles for febrile neutropenia and neutropenic infection [see Dosage and Administration (2.7), Adverse Reactions (6)].

5.4 Enterocolitis and Neutropenic Colitis

Enterocolitis and neutropenic colitis (typhlitis) have occurred in patients treated with DOCETAXEL INJECTION alone and in combination with other chemotherapeutic agents, despite the coadministration of G-CSF. Caution is recommended for patients with neutropenia, particularly at risk for developing gastrointestinal complications. Enterocolitis and neutropenic enterocolitis may develop at any time, and could lead to death as early as the first day of symptom onset. Monitor patients closely from onset of any symptoms of gastrointestinal toxicity. Inform patients to contact their healthcare provider with new, or worsening symptoms of gastrointestinal toxicity [see Dosage and Administration (2), Warnings and Precautions (5.3), Adverse Reactions (6.2)].

5.5 Hypersensitivity Reactions

Monitor patients closely for hypersensitivity reactions, especially during the first and second infusions. Severe hypersensitivity reactions characterized by generalized rash/erythema, hypotension and/or bronchospasm, or fatal anaphylaxis, have been reported in patients premedicated with 3 days of corticosteroids. Severe hypersensitivity reactions require immediate discontinuation of the DOCETAXEL INJECTION infusion and aggressive therapy. Do not rechallenge patients with a history of severe hypersensitivity reactions with DOCETAXEL INJECTION [see Contraindications (4)].

Patients who have previously experienced a hypersensitivity reaction to paclitaxel may develop a hypersensitivity reaction to docetaxel that may include severe or fatal reactions such as anaphylaxis. Monitor patients with a previous history of hypersensitivity to paclitaxel closely during initiation of DOCETAXEL INJECTION therapy. Hypersensitivity reactions may occur within a few minutes following initiation of a DOCETAXEL INJECTION infusion. If minor reactions such as flushing or localized skin reactions occur, interruption of therapy is not required. All patients should be premedicated with an oral corticosteroid prior to the initiation of the infusion of DOCETAXEL INJECTION [see Dosage and Administration (2.6)].

5.6 Fluid Retention

Severe fluid retention has been reported following docetaxel therapy. Patients should be premedicated with oral corticosteroids prior to each DOCETAXEL INJECTION administration to reduce the incidence and severity of fluid retention [see Dosage and Administration (2.6)]. Patients with preexisting effusions should be closely monitored from the first dose for the possible exacerbation of the effusions.

When fluid retention occurs, peripheral edema usually starts in the lower extremities and may become generalized with a median weight gain of 2 kg.

Among 92 breast cancer patients premedicated with 3-day corticosteroids, moderate fluid retention occurred in 27.2% and severe fluid retention in 6.5%. The median cumulative dose to onset of moderate or severe fluid retention was 819 mg/m^2. Nine of 92 patients (9.8%) of patients discontinued treatment due to fluid retention: 4 patients discontinued with severe fluid retention; the remaining 5 had mild or moderate fluid retention. The median cumulative dose to treatment discontinuation due to fluid retention was 1021 mg/m^2. Fluid retention was completely, but sometimes slowly, reversible with a median of 16 weeks from the last infusion of docetaxel to resolution (range: 0 to 42+ weeks). Patients developing peripheral edema may be treated with standard measures, e.g., salt restriction, oral diuretic(s).

5.7 Second Primary Malignancies

Second primary malignancies, notably acute myeloid leukemia (AML), myelodysplastic syndrome (MDS), Non-Hodgkin’s Lymphoma (NHL), and renal cancer, have been reported in patients treated with docetaxel-containing regimens. These adverse reactions may occur several months or years after docetaxel-containing therapy.

Treatment-related AML or MDS has occurred in patients given anthracyclines and/or cyclophosphamide, including use in adjuvant therapy for breast cancer. In the adjuvant breast cancer trial (TAX316) AML occurred in 3 of 744 patients who received docetaxel (T), doxorubicin and cyclophosphamide (TAC) and in 1 of 736 patients who received fluorouracil, doxorubicin, and cyclophosphamide [see Clinical Studies (14.2)]. In TAC-treated patients, the risk of delayed myelodysplasia or myeloid leukemia requires hematological follow-up. Monitor patients for second primary malignancies [see Adverse Reactions (6.1)].

5.8 Cutaneous Reactions

Localized erythema of the extremities with edema followed by desquamation has been observed. In case of severe skin toxicity, an adjustment in dosage is recommended [see Dosage and Administration (2.7)]. The discontinuation rate due to skin toxicity was 1.6% (15/965) for metastatic breast cancer patients. Among 92 breast cancer patients premedicated with 3-day corticosteroids, there were no cases of severe skin toxicity reported and no patient discontinued docetaxel due to skin toxicity.

Severe cutaneous adverse reactions (SCARs) such as Stevens-Johnson syndrome (SJS), toxic epidermal necrolysis (TEN), and acute generalized exanthematous pustulosis (AGEP) have been reported in association with docetaxel treatment. Patients should be informed about the signs and symptoms of serious skin manifestations and monitored closely. Permanent treatment discontinuation should be considered in patients who experience SCARs.

5.9 Neurologic Reactions

Severe neurosensory symptoms (e.g., paresthesia, dysesthesia, pain) were observed in 5.5% (53/965) of metastatic breast cancer patients, and resulted in treatment discontinuation in 6.1%. When these symptoms occur, dosage must be adjusted. If symptoms persist, treatment should be discontinued [see Dosage and Administration (2.7)]. Patients who experienced neurotoxicity in clinical trials and for whom follow-up information on the complete resolution of the event was available had spontaneous reversal of symptoms with a median of 9 weeks from onset (range: 0 to 106 weeks). Severe peripheral motor neuropathy mainly manifested as distal extremity weakness occurred in 4.4% (42/965).

5.10 Eye Disorders

Cystoid macular edema (CME) has been reported in patients treated with docetaxel. Patients with impaired vision should undergo a prompt and comprehensive ophthalmologic examination. If CME is diagnosed, DOCETAXEL INJECTION treatment should be discontinued and appropriate treatment initiated. Alternative non-taxane cancer treatment should be considered.

5.11 Asthenia

Severe asthenia has been reported in 14.9% (144/965) of metastatic breast cancer patients but has led to treatment discontinuation in only 1.8%. Symptoms of fatigue and weakness may last a few days up to several weeks and may be associated with deterioration of performance status in patients with progressive disease.

5.12 Embryo-Fetal Toxicity

Based on findings from animal reproduction studies and its mechanism of action, DOCETAXEL INJECTION can cause fetal harm when administered to a pregnant woman [see Clinical Pharmacology (12.1)]. Available data from case reports in the literature and pharmacovigilance with docetaxel use in pregnant women are not sufficient to inform the drug-associated risk of major birth defects, miscarriage or adverse maternal or fetal outcomes. In animal reproduction studies, administration of docetaxel to pregnant rats and rabbits during the period of organogenesis caused embryo-fetal toxicities, including intrauterine mortality, at doses as low as 0.02 and 0.003 times the recommended human dose based on body surface area, respectively.

Advise pregnant women and females of reproductive potential of the potential risk to a fetus. Verify pregnancy status in females of reproductive potential prior to initiating DOCETAXEL INJECTION. Advise females of reproductive potential to use effective contraception during treatment and for 6 months after the last dose of DOCETAXEL INJECTION. Advise male patients with female partners of reproductive potential to use effective contraception during treatment and for 3 months after the last dose of DOCETAXEL INJECTION [see Use in Specific Populations (8.1, 8.3)].

5.13 Alcohol Content

Cases of intoxication have been reported with some formulations of docetaxel due to the alcohol content. The alcohol content in a dose of DOCETAXEL INJECTION may affect the central nervous system and should be taken into account for patients in whom alcohol intake should be avoided or minimized. Consideration should be given to the alcohol content in DOCETAXEL INJECTION on the ability to drive or use machines immediately after the infusion. Each administration of DOCETAXEL INJECTION at 100 mg/m^2 delivers 2.0 g/m^2 of ethanol. For a patient with a BSA of 2.0 m^2, this would deliver 4.0 grams of ethanol [see Description (11)]. Other docetaxel products may have a different amount of alcohol.

5.14 Tumor Lysis Syndrome

Tumor lysis syndrome has been reported with docetaxel [see Adverse Reactions (6.2)]. Patients at risk of tumor lysis syndrome (e.g., with renal impairment, hyperuricemia, bulky tumor) should be closely monitored prior to initiating DOCETAXEL INJECTION and periodically during treatment. Correction of dehydration and treatment of high uric acid levels are recommended prior to initiation of treatment.

6 ADVERSE REACTIONS

The most serious adverse reactions from docetaxel are:

- Toxic Deaths [see Boxed Warning, Warnings and Precautions (5.1)]
- Hepatic Impairment [see Boxed Warning, Warnings and Precautions (5.2)]
- Hematologic Effects [see Boxed Warning, Warnings and Precautions (5.3)]
- Enterocolitis and Neutropenic Colitis [see Warnings and Precautions (5.4)]
- Hypersensitivity Reactions [see Boxed Warning, Warnings and Precautions (5.5)]
- Fluid Retention [see Boxed Warning, Warnings and Precautions (5.6)]
- Second Primary Malignancies [see Warnings and Precautions (5.7)]
- Cutaneous Reactions [see Warnings and Precautions (5.8)]
- Neurologic Reactions [see Warnings and Precautions (5.9)]
- Eye Disorders [see Warnings and Precautions (5.10)]
- Asthenia [see Warnings and Precautions (5.11)]
- Alcohol Content [see Warnings and Precautions (5.13)]

The most common adverse reactions across all docetaxel indications are infections, neutropenia, anemia, febrile neutropenia, hypersensitivity, thrombocytopenia, neuropathy, dysgeusia, dyspnea, constipation, anorexia, nail disorders, fluid retention, asthenia, pain, nausea, diarrhea, vomiting, mucositis, alopecia, skin reactions, and myalgia. Incidence varies depending on the indication.

Adverse reactions are described according to indication. Because clinical trials are conducted under widely varying conditions, adverse reaction rates observed in the clinical trials of a drug cannot be directly compared to rates in the clinical trials of another drug and may not reflect the rates observed in practice.

Responding patients may not experience an improvement in performance status on therapy and may experience worsening. The relationship between changes in performance status, response to therapy, and treatment-related side effects has not been established.

6.1 Clinical Trials Experience

Breast Cancer
Monotherapy with docetaxel for locally advanced or metastatic breast cancer after failure of prior chemotherapy
Docetaxel 100 mg/m^2 : Adverse drug reactions occurring in at least 5% of patients are compared for three populations who received docetaxel administered at 100 mg/m^2 as a 1-hour infusion every 3 weeks: 2045 patients with various tumor types and normal baseline liver function tests; the subset of 965 patients with locally advanced or metastatic breast cancer, both previously treated and untreated with chemotherapy, who had normal baseline liver function tests; and an additional 61 patients with various tumor types who had abnormal liver function tests at baseline. These reactions were described using COSTART terms and were considered possibly or probably related to docetaxel. At least 95% of these patients did not receive hematopoietic support. The safety profile is generally similar in patients receiving docetaxel for the treatment of breast cancer and in patients with other tumor types (See Table 3).
Table 3 - Summary of Adverse Reactions in Patients Receiving Docetaxel at 100 mg/m^2

Adverse Reaction | All Tumor Types Normal LFTs* n=2045 % | All Tumor Types Elevated LFTs** n=61 % | Breast Cancer Normal LFTs* n=965 %
Hematologic Neutropenia <2000 cells/mm^3 <500 cells/mm^3 | 96 75 | 96 88 | 99 86
Leukopenia <4000 cells/mm^3 <1,000 cells/mm^3 | 96 32 | 98 47 | 99 44
Thrombocytopenia <100,000 cells/mm^3 | 8 | 25 | 9
Anemia <11 g/dL <8 g/dL | 90 9 | 92 31 | 94 8
Febrile Neutropenia*** | 11 | 26 | 12
Septic Death Non-Septic Death | 2 1 | 5 7 | 1 1
Infections Any Severe | 22 6 | 33 16 | 22 6
Fever in Absence of Infection Any Severe | 31 2 | 41 8 | 35 2
Hypersensitivity Reactions Regardless of Premedication Any Severe With 3-day Premedication Any Severe | 21 4 n=92 15 2 | 20 10 n=3 33 0 | 18 3 n=92 15 2
Fluid Retention Regardless of Premedication Any Severe With 3-day Premedication Any Severe | 47 7 n=92 64 7 | 39 8 n=3 67 33 | 60 9 n=92 64 7
Neurosensory Any Severe | 49 4 | 34 0 | 58 6
Cutaneous Any Severe | 48 5 | 54 10 | 47 5
Nail Changes Any Severe | 31 3 | 23 5 | 41 4
Gastrointestinal Nausea Vomiting Diarrhea Severe | 39 22 39 5 | 38 23 33 5 | 42 23 43 6
Stomatitis Any Severe | 42 6 | 49 13 | 52 7
Alopecia | 76 | 62 | 74
Asthenia Any Severe | 62 13 | 53 25 | 66 15
Myalgia Any Severe | 19 2 | 16 2 | 21 2
Arthralgia | 9 | 7 | 8
Infusion Site Reactions | 4 | 3 | 4

*Normal Baseline LFTs: Transaminases ≤1.5 times ULN or alkaline phosphatase ≤ 2.5 times ULN or isolated elevations of transaminases or alkaline phosphatase up to 5 times ULN
**Elevated Baseline LFTs: AST and/or ALT >1.5 times ULN concurrent with alkaline phosphatase > 2.5 times ULN
***Febrile Neutropenia: ANC grade 4 with fever >38oC with intravenous antibiotics and/or hospitalization

Hematologic reactions

Reversible marrow suppression was the major dose-limiting toxicity of docetaxel [see Warnings and Precautions (5.3)]. The median time to nadir was 7 days, while the median duration of severe neutropenia (<500 cells/mm^3) was 7 days. Among 2045 patients with solid tumors and normal baseline LFTs, severe neutropenia occurred in 75.4% and lasted for more than 7 days in 2.9% of cycles.

Febrile neutropenia (<500 cells/mm^3 with fever > 38°C with intravenous antibiotics and/or hospitalization) occurred in 11% of patients with solid tumors, in 12.3% of patients with metastatic breast cancer, and in 9.8% of 92 breast cancer patients premedicated with 3-day corticosteroids.

Severe infectious episodes occurred in 6.1% of patients with solid tumors, in 6.4% of patients with metastatic breast cancer, and in 5.4% of 92 breast cancer patients premedicated with 3-day corticosteroids.

Thrombocytopenia (<100,000 cells/mm^3) associated with fatal gastrointestinal hemorrhage has been reported.

Hypersensitivity reactions

Severe hypersensitivity reactions have been reported [see Boxed Warning, Warnings and Precautions (5.5)]. Minor events, including flushing, rash with or without pruritus, chest tightness, back pain, dyspnea, drug fever, or chills, have been reported and resolved after discontinuing the infusion and instituting appropriate therapy.

Fluid retention

Fluid retention can occur with the use of DOCETAXEL INJECTION [see Boxed Warning, Dosage and Administration (2.6), Warnings and Precautions (5.6)].

Cutaneous reactions

Severe skin toxicity is discussed elsewhere in the label [see Warnings and Precautions (5.8)]. Reversible cutaneous reactions characterized by a rash including localized eruptions, mainly on the feet and/or hands, but also on the arms, face, or thorax, usually associated with pruritus, have been observed. Eruptions generally occurred within 1 week after docetaxel infusion, recovered before the next infusion, and were not disabling.

Severe nail disorders were characterized by hypo or hyperpigmentation, and occasionally by onycholysis (in 0.8% of patients with solid tumors) and pain.

Neurologic reactions

Neurologic reactions are discussed elsewhere in the label [seeWarnings and Precautions (5.9)].

Gastrointestinal reactions

Nausea, vomiting, and diarrhea were generally mild to moderate. Severe reactions occurred in 3% to 5% of patients with solid tumors and to a similar extent among metastatic breast cancer patients. The incidence of severe reactions was 1% or less for the 92 breast cancer patients premedicated with 3-day corticosteroids.

Severe stomatitis occurred in 5.5% of patients with solid tumors, in 7.4% of patients with metastatic breast cancer, and in 1.1% of the 92 breast cancer patients premedicated with 3-day corticosteroids.

Cardiovascular reactions

Hypotension occurred in 2.8% of patients with solid tumors; 1.2% required treatment. Clinically meaningful events such as heart failure, sinus tachycardia, atrial flutter, dysrhythmia, unstable angina, pulmonary edema, and hypertension have occurred. Seven of 86 (8.1%) of metastatic breast cancer patients receiving docetaxel 100 mg/m^2 in a randomized trial and who had serial left ventricular ejection fractions assessed developed deterioration of LVEF by ≥ 10% associated with a drop below the institutional lower limit of normal.

Infusion site reactions

Infusion site reactions were generally mild and consisted of hyperpigmentation, inflammation, redness or dryness of the skin, phlebitis, extravasation, or swelling of the vein.

Hepatic reactions

In patients with normal LFTs at baseline, bilirubin values greater than the ULN occurred in 8.9% of patients. Increases in AST or ALT > 1.5 times the ULN, or alkaline phosphatase > 2.5 times ULN, were observed in 18.9% and 7.3% of patients, respectively. While on docetaxel, increases in AST and/or ALT > 1.5 times ULN concomitant with alkaline phosphatase > 2.5 times ULN occurred in 4.3% of patients with normal LFTs at baseline. Whether these changes were related to the drug or underlying disease has not been established.

Hematologic and other toxicity: Relation to dose and baseline liver chemistry abnormalities
Hematologic and other toxicity is increased at higher doses and in patients with elevated baseline liver function tests (LFTs). In the following tables, adverse drug reactions are compared for three populations: 730 patients with normal LFTs given docetaxel at 100 mg/m^2 in the randomized and single arm studies of metastatic breast cancer after failure of previous chemotherapy; 18 patients in these studies who had abnormal baseline LFTs (defined as AST and/or ALT > 1.5 times ULN concurrent with alkaline phosphatase > 2.5 times ULN); and 174 patients in Japanese studies given docetaxel at 60 mg/m^2 who had normal LFTs (see Tables 4 and 5).
Table 4 - Hematologic Adverse Reactions in Breast Cancer Patients Previously Treated with Chemotherapy Treated at Docetaxel 100 mg/m^2 with Normal or Elevated Liver Function Tests or 60 mg/m^2 with Normal Liver Function Tests

Adverse Reaction | Docetaxel 100 mg/m^2 |  | Docetaxel 60 mg/m^2
Adverse Reaction | Normal LFTs* n=730 % | Elevated LFTs** n=18 % | Normal LFTs* n=174 %
Neutropenia Any <2000 cells/mm^3 Grade 4 <500 cells/mm^3 | 98 84 | 100 94 | 95 75
Thrombocytopenia Any <100,000 cells/mm^3 Grade 4 <20,000 cells/mm^3 | 11 1 | 44 17 | 14 1
Anemia <11 g/dL | 95 | 94 | 65
Infection*** Any Grade 3 and 4 | 23 7 | 39 33 | 1 0
Febrile Neutropenia**** By Patient By Course | 12 2 | 33 9 | 0 0
Septic Death | 2 | 6 | 1
Non-Septic Death | 1 | 11 | 0

*Normal Baseline LFTs: Transaminases ≤ 1.5 times ULN or alkaline phosphatase ≤ 2.5 times ULN or isolated elevations of transaminases or alkaline phosphatase up to 5 times ULN
**Elevated Baseline LFTs: AST and/or ALT > 1.5 times ULN concurrent with alkaline phosphatase > 2.5 times ULN
***Incidence of infection requiring hospitalization and/or intravenous antibiotics was 8.5% (n=62) among the 730 patients with normal LFTs at baseline; 7 patients had concurrent grade 3 neutropenia, and 46 patients had grade 4 neutropenia.
****Febrile Neutropenia: For 100 mg/m^2, ANC grade 4 and fever > 38°C with intravenous antibiotics and/or hospitalization; for 60 mg/m^2 , ANC grade 3/4 and fever > 38.1°C
Table 5 - Non-Hematologic Adverse Reactions in Breast Cancer Patients Previously Treated with Chemotherapy Treated at Docetaxel 100 mg/m^2 with Normal or Elevated Liver Function Tests or 60 mg/m^2 with Normal Liver Function Tests

Adverse Reaction | Docetaxel 100 mg/m^2 |  | Docetaxel 60 mg/m^2
Adverse Reaction | Normal LFTs* n=730 % | Elevated LFTs** n=18 % | Normal LFTs* n=174 %
Acute Hypersensitivity Reaction Regardless of Premedication Any Severe | 13 1 | 6 0 | 1 0
Fluid Retention*** Regardless of Premedication Any Severe | 56 8 | 61 17 | 13 0
Neurosensory Any Severe | 57 6 | 50 0 | 20 0
Myalgia | 23 | 33 | 3
Cutaneous Any Severe | 45 5 | 61 17 | 31 0
Asthenia Any Severe | 65 17 | 44 22 | 66 0
Diarrhea Any Severe | 42 6 | 28 11 | NA
Stomatitis Any Severe | 53 8 | 67 39 | 19 1

*Normal Baseline LFTs: Transaminases ≤ 1.5 times ULN or alkaline phosphatase ≤ 2.5 times ULN or isolated elevations of transaminases or alkaline phosphatase up to 5 times ULN
** Elevated Baseline Liver Function: AST and/or ALT > 1.5 times ULN concurrent with alkaline phosphatase > 2.5 times ULN
***Fluid Retention includes (by COSTART): edema (peripheral, localized, generalized, lymphedema, pulmonary edema, and edema otherwise not specified) and effusion (pleural, pericardial, and ascites); no premedication given with the 60 mg/m^2 dose
NA = not available

In the three-arm monotherapy trial, TAX313, which compared docetaxel 60 mg/m^2 , 75 mg/m^2 and 100 mg/m^2 in advanced breast cancer, grade 3/4 or severe adverse reactions occurred in 49.0% of patients treated with docetaxel 60 mg/m^2 compared to 55.3% and 65.9% treated with 75 mg/m^2 and 100 mg/m^2 respectively. Discontinuation due to adverse reactions was reported in 5.3% of patients treated with 60 mg/m^2 versus 6.9% and 16.5% for patients treated at 75 mg/m^2 and 100 mg/m^2 respectively. Deaths within 30 days of last treatment occurred in 4.0% of patients treated with 60 mg/m^2 compared to 5.3% and 1.6% for patients treated at 75 mg/m^2 and 100 mg/m^2 respectively.

The following adverse reactions were associated with increasing docetaxel doses: fluid retention (26%, 38%, and 46% at 60 mg/m^2, 75 mg/m^2 , and 100 mg/m^2 respectively), thrombocytopenia (7%, 11% and 12% respectively), neutropenia (92%, 94%, and 97% respectively), febrile neutropenia (5%, 7%, and 14% respectively), treatment-related grade 3/4 infection (2%, 3%, and 7% respectively) and anemia (87%, 94%, and 97% respectively).

Combination therapy with docetaxel in the adjuvant treatment of breast cancer

The following table presents treatment-emergent adverse reactions observed in 744 patients, who were treated with docetaxel 75 mg/m² every 3 weeks in combination with doxorubicin and cyclophosphamide (see Table 6).
Table 6 - Clinically Important Treatment-Emergent Adverse Reactions Regardless of Causal Relationship in Patients Receiving Docetaxel in Combination with Doxorubicin and Cyclophosphamide (TAX316)

 | Docetaxel 75 mg/m^2+ Doxorubicin 50 mg/m^2+ Cyclophosphamide 500 mg/m^2 (TAC) n=744 % |  | Fluorouracil 500 mg/m^2+ Doxorubicin 50 mg/m^2+ Cyclophosphamide 500 mg/m^2 (FAC) n=736 %
Adverse Reaction | Any | Grade 3/4 | Any | Grade 3/4
Anemia | 92 | 4 | 72 | 2
Neutropenia | 71 | 66 | 82 | 49
Fever in absence of infection | 47 | 1 | 17 | 0
Infection | 39 | 4 | 36 | 2
Thrombocytopenia | 39 | 2 | 28 | 1
Febrile neutropenia | 25 | N/A | 3 | N/A
Neutropenic infection | 12 | N/A | 6 | N/A
Hypersensitivity reactions | 13 | 1 | 4 | 0
Lymphedema | 4 | 0 | 1 | 0
Fluid Retention* Peripheral edema Weight gain | 35 27 13 | 1 0 0 | 15 7 9 | 0 0 0
Neuropathy sensory | 26 | 0 | 10 | 0
Neuro-cortical | 5 | 1 | 6 | 1
Neuropathy motor | 4 | 0 | 2 | 0
Neuro-cerebellar | 2 | 0 | 2 | 0
Syncope | 2 | 1 | 1 | 0
Alopecia | 98 | N/A | 97 | N/A
Skin toxicity | 27 | 1 | 18 | 0
Nail disorders | 19 | 0 | 14 | 0
Nausea | 81 | 5 | 88 | 10
Stomatitis | 69 | 7 | 53 | 2
Vomiting | 45 | 4 | 59 | 7
Diarrhea | 35 | 4 | 28 | 2
Constipation | 34 | 1 | 32 | 1
Taste perversion | 28 | 1 | 15 | 0
Anorexia | 22 | 2 | 18 | 1
Abdominal Pain | 11 | 1 | 5 | 0
Amenorrhea | 62 | N/A | 52 | N/A
Cough | 14 | 0 | 10 | 0
Cardiac dysrhythmias | 8 | 0 | 6 | 0
Vasodilatation | 27 | 1 | 21 | 1
Hypotension | 2 | 0 | 1 | 0
Phlebitis | 1 | 0 | 1 | 0
Asthenia | 81 | 11 | 71 | 6
Myalgia | 27 | 1 | 10 | 0
Arthralgia | 19 | 1 | 9 | 0
Lacrimation disorder | 11 | 0 | 7 | 0
Conjunctivitis | 5 | 0 | 7 | 0

* COSTART term and grading system for events related to treatment.

Of the 744 patients treated with TAC, 36.3% experienced severe treatment-emergent adverse reactions compared to 26.6% of the 736 patients treated with FAC. Dose reductions due to hematologic toxicity occurred in 1% of cycles in the TAC arm versus 0.1% of cycles in the FAC arm. Six percent of patients treated with TAC discontinued treatment due to adverse reactions, compared to 1.1% treated with FAC; fever in the absence of infection and allergy being the most common reasons for withdrawal among TAC-treated patients. Two patients died in each arm within 30 days of their last study treatment; 1 death per arm was attributed to study drugs.

Fever and infection

During the treatment period, fever in the absence of infection was seen in 46.5% of TAC-treated patients and in 17.1% of FAC-treated patients. Grade 3/4 fever in the absence of infection was seen in 1.3% and 0% of TAC and FAC-treated patients, respectively. Infection was seen in 39.4% of TAC-treated patients compared to 36.3% of FAC-treated patients. Grade 3/4 infection was seen in 3.9% and 2.2% of TAC-treated and FAC-treated patients, respectively. There were no septic deaths in either treatment arm during the treatment period.

Gastrointestinal reactions

In addition to gastrointestinal reactions reflected in the table above, 7 patients in the TAC arm were reported to have colitis/enteritis/large intestine perforation versus one patient in the FAC arm. Five of the 7 TAC-treated patients required treatment discontinuation; no deaths due to these events occurred during the treatment period.

Cardiovascular reactions

More cardiovascular reactions were reported in the TAC arm versus the FAC arm during the treatment period: arrhythmias, all grades (6.2% vs 4.9%), and hypotension, all grades (1.9% vs 0.8%). Twenty-six (26) patients (3.5%) in the TAC arm and 17 patients (2.3%) in the FAC arm developed CHF during the study period. All except one patient in each arm were diagnosed with CHF during the follow-up period. Two (2) patients in TAC arm and 4 patients in FAC arm died due to CHF. The risk of CHF was higher in the TAC arm in the first year, and then was similar in both treatment arms.

Adverse reactions during the follow-up period (median follow-up time of 8 years)

In study TAX316, the most common adverse reactions that started during the treatment period and persisted into the follow-up period in TAC and FAC patients are described below (median follow-up time of 8 years).

Nervous system disorders

In study TAX316, peripheral sensory neuropathy started during the treatment period and persisted into the follow-up period in 84 patients (11.3%) in TAC arm and 15 patients (2%) in FAC arm. At the end of the follow-up period (median follow-up time of 8 years), peripheral sensory neuropathy was observed to be ongoing in 10 patients (1.3%) in TAC arm, and in 2 patients (0.3%) in FAC arm.

Skin and subcutaneous tissue disorders

In study TAX316, alopecia persisting into the follow-up period after the end of chemotherapy was reported in 687 of 744 TAC patients (92.3%) and 645 of 736 FAC patients (87.6%). At the end of the follow-up period (actual median follow-up time of 8 years), alopecia was observed to be ongoing in 29 TAC patients (3.9%) and 16 FAC patients (2.2%).

Reproductive system and breast disorders

In study TAX316, amenorrhea that started during the treatment period and persisted into the follow-up period after the end of chemotherapy was reported in 202 of 744 TAC patients (27.2%) and 125 of 736 FAC patients (17.0%). Amenorrhea was observed to be ongoing at the end of the follow-up period (median follow-up time of 8 years) in 121 of 744 TAC patients (16.3%) and 86 FAC patients (11.7%).

General disorders and administration site conditions

In study TAX316, peripheral edema that started during the treatment period and persisted into the follow-up period after the end of chemotherapy was observed in 119 of 744 TAC patients (16.0%) and 23 of 736 FAC patients (3.1%). At the end of the follow-up period (actual median follow-up time of 8 years), peripheral edema was ongoing in 19 TAC patients (2.6%) and 4 FAC patients (0.5%).

In study TAX316, lymphedema that started during the treatment period and persisted into the follow-up period after the end of chemotherapy was reported in 11 of 744 TAC patients (1.5%) and 1 of 736 FAC patients (0.1%). At the end of the follow-up period (actual median follow-up time of 8 years), lymphedema was observed to be ongoing in 6 TAC patients (0.8%) and 1 FAC patient (0.1%).

In study TAX316, asthenia that started during the treatment period and persisted into the follow-up period after the end of chemotherapy was reported in 236 of 744 TAC patients (31.7%) and 180 of 736 FAC patients (24.5%). At the end of the follow-up period (actual median follow-up time of 8 years), asthenia was observed to be ongoing in 29 TAC patients (3.9%) and 16 FAC patients (2.2%).

Acute myeloid leukemia (AML) /Myelodysplastic syndrome (MDS)

AML occurred in the adjuvant breast cancer trial (TAX316). The cumulative risk of developing treatment-related AML at median follow-up time of 8 years in TAX316 was 0.4% for TAC-treated patients and 0.1% for FAC-treated patients. One TAC patient (0.1%) and 1 FAC patient (0.1%) died due to AML during the follow-up period (median follow-up time of 8 years). Myelodysplastic syndrome occurred in 2 of 744 (0.3%) patients who received TAC and in 1 of 736 (0.1%) patients who received FAC. AML occurs at a higher frequency when these agents are given in combination with radiation therapy.
Lung Cancer

Monotherapy with docetaxel for unresectable, locally advanced or metastatic NSCLC previously treated with platinum-based chemotherapy

Docetaxel 75 mg/m^2: Treatment-emergent adverse drug reactions are shown in Table 7. Included in this table are safety data for a total of 176 patients with non-small cell lung carcinoma and a history of prior treatment with platinum-based chemotherapy who were treated in two randomized, controlled trials. These reactions were described using NCI Common Toxicity Criteria regardless of relationship to study treatment, except for the hematologic toxicities or where otherwise noted.

Table 7 – Treatment-Emergent Adverse Reactions Regardless of Relationship to Treatment in Patients Receiving Docetaxel as Monotherapy for Non-small Cell Lung Cancer Previously Treated with Platinum-Based Chemotherapy*

Adverse Reaction | Docetaxel 75 mg/m^2 n=176 % | Best Supportive Care n=49 % | Vinorelbine/ Ifosfamide n=119 %
Neutropenia Any Grade 3/4 | 84 65 | 14 12 | 83 57
Leukopenia Any Grade 3/4 | 84 49 | 6 0 | 89 43
Thrombocytopenia Any Grade 3/4 | 8 3 | 0 0 | 8 2
Anemia Any Grade 3/4 | 91 9 | 55 12 | 91 14
Febrile Neutropenia** | 6 | NA† | 1
Infection Any Grade 3/4 | 34 10 | 29 6 | 30 9
Treatment Related Mortality | 3 | NA† | 3
Hypersensitivity Reactions Any Grade 3/4 | 6 3 | 0 0 | 1 0
Fluid Retention Any Severe | 34 3 | ND†† | 23 3
Neurosensory Any Grade 3/4 | 23 2 | 14 6 | 29 5
Neuromotor Any Grade 3/4 | 16 5 | 8 6 | 10 3
Skin Any Grade 3/4 | 20 1 | 6 2 | 17 1
Gastrointestinal Nausea Any Grade 3/4 Vomiting Any Grade 3/4 Diarrhea Any Grade 3/4 | 34 5 22 3 23 3 | 31 4 27 2 6 0 | 31 8 22 6 12 4
Alopecia | 56 | 35 | 50
Asthenia Any Severe*** | 53 18 | 57 39 | 54 23
Stomatitis Any Grade 3/4 | 26 2 | 6 0 | 8 1
Pulmonary Any Grade 3/4 | 41 21 | 49 29 | 45 19
Nail Disorder Any Severe*** | 11 1 | 0 0 | 2 0
Myalgia Any Severe*** | 6 0 | 0 0 | 3 0
Arthralgia Any Severe*** | 3 0 | 2 0 | 2 1
Taste Perversion Any Severe*** | 6 1 | 0 0 | 0 0

*Normal Baseline LFTs: Transaminases ≤ 1.5 times ULN or alkaline phosphatase ≤ 2.5 times ULN or isolated elevations of transaminases or alkaline phosphatase up to 5 times ULN
**Febrile Neutropenia: ANC grade 4 with fever >38°C with intravenous antibiotics and/or hospitalization
***COSTART term and grading system
†Not Applicable
†† Not Done
Combination therapy with docetaxel in chemotherapy-naive advanced unresectable or metastatic NSCLC
Table 8 presents safety data from two arms of an open label, randomized controlled trial (TAX326) that enrolled patients with unresectable stage IIIB or IV non-small cell lung cancer and no history of prior chemotherapy. Adverse reactions were described using the NCI Common Toxicity Criteria except where otherwise noted.
Table 8 - Adverse Reactions Regardless of Relationship to Treatment in Chemotherapy-Naive Advanced Non-small Cell Lung Cancer Patients Receiving Docetaxel in Combination with Cisplatin

Adverse Reaction | Docetaxel 75 mg/m^2 + Cisplatin 75 mg/m^2 n=406 % | Vinorelbine 25 mg/m^2 + Cisplatin 100 mg/m^2 n=396 %
Neutropenia Any Grade 3/4 | 91 74 | 90 78
Febrile Neutropenia | 5 | 5
Thrombocytopenia Any Grade 3/4 | 15 3 | 15 4
Anemia Any Grade 3/4 | 89 7 | 94 25
Infection Any Grade 3/4 | 35 8 | 37 8
Fever in absence of infection Any Grade 3/4 | 33 < 1 | 29 1
Hypersensitivity Reaction* Any Grade 3/4 | 12 3 | 4 < 1
Fluid Retention** Any All severe or life-threatening events | 54 2 | 42 2
Pleural effusion Any All severe or life-threatening events | 23 2 | 22 2
Peripheral edema Any All severe or life-threatening events | 34 <1 | 18 <1
Weight gain Any All severe or life-threatening events | 15 <1 | 9 <1
Neurosensory Any Grade 3/4 | 47 4 | 42 4
Neuromotor Any Grade 3/4 | 19 3 | 17 6
Skin Any Grade 3/4 | 16 <1 | 14 1
Nausea Any Grade 3/4 | 72 10 | 76 17
Vomiting Any Grade 3/4 | 55 8 | 61 16
Diarrhea Any Grade 3/4 | 47 7 | 25 3
Anorexia** Any All severe or life-threatening events | 42 5 | 40 5
Stomatitis Any Grade 3/4 | 24 2 | 21 1
Alopecia Any Grade 3 | 75 <1 | 42 0
Asthenia** Any All severe or life-threatening events | 74 12 | 75 14
Nail Disorder** Any All severe events | 14 <1 | <1 0
Myalgia** Any All severe events | 18 <1 | 12 <1

* Replaces NCI term “Allergy”

** COSTART term and grading system
Deaths within 30 days of last study treatment occurred in 31 patients (7.6%) in the docetaxel+cisplatin arm and 37 patients (9.3%) in the vinorelbine+cisplatin arm. Deaths within 30 days of last study treatment attributed to study drug occurred in 9 patients (2.2%) in the docetaxel+cisplatin arm and 8 patients (2.0%) in the vinorelbine+cisplatin arm.

The second comparison in the study, vinorelbine+cisplatin versus docetaxel+carboplatin (which did not demonstrate a superior survival associated with docetaxel [see Clinical Studies (14.3)]) demonstrated a higher incidence of thrombocytopenia, diarrhea, fluid retention, hypersensitivity reactions, skin toxicity, alopecia and nail changes on the docetaxel+carboplatin arm, while a higher incidence of anemia, neurosensory toxicity, nausea, vomiting, anorexia and asthenia was observed on the vinorelbine+cisplatin arm.
Prostate Cancer

Combination therapy with docetaxel in patients with prostate cancer

The following data are based on the experience of 332 patients, who were treated with docetaxel 75 mg/m² every 3 weeks in combination with prednisone 5 mg orally twice daily (see Table 9).
Table 9 - Clinically Important Treatment-Emergent Adverse Reactions (Regardless of Relationship) in Patients with Prostate Cancer Who Received Docetaxel in Combination with Prednisone (TAX327)

 | Docetaxel 75 mg/m^2 every 3 weeks + prednisone 5 mg twice daily n=332 % |  | Mitoxantrone 12 mg/m^2 every 3 weeks + prednisone 5 mg twice daily n=335 %
Adverse Reaction | Any | Grade 3/4 | Any | Grade 3/4
Anemia | 67 | 5 | 58 | 2
Neutropenia | 41 | 32 | 48 | 22
Thrombocytopenia | 3 | 1 | 8 | 1
Febrile neutropenia | 3 | N/A | 2 | N/A
Infection | 32 | 6 | 20 | 4
Epistaxis | 6 | 0 | 2 | 0
Allergic Reactions | 8 | 1 | 1 | 0
Fluid Retention* Weight Gain* Peripheral Edema* | 24 8 18 | 1 0 0 | 5 3 2 | 0 0 0
Neuropathy Sensory | 30 | 2 | 7 | 0
Neuropathy Motor | 7 | 2 | 3 | 1
Rash/Desquamation | 6 | 0 | 3 | 1
Alopecia | 65 | N/A | 13 | N/A
Nail Changes | 30 | 0 | 8 | 0
Nausea | 41 | 3 | 36 | 2
Diarrhea | 32 | 2 | 10 | 1
Stomatitis/Pharyngitis | 20 | 1 | 8 | 0
Taste Disturbance | 18 | 0 | 7 | 0
Vomiting | 17 | 2 | 14 | 2
Anorexia | 17 | 1 | 14 | 0
Cough | 12 | 0 | 8 | 0
Dyspnea | 15 | 3 | 9 | 1
Cardiac left ventricular function | 10 | 0 | 22 | 1
Fatigue | 53 | 5 | 35 | 5
Myalgia | 15 | 0 | 13 | 1
Tearing | 10 | 1 | 2 | 0
Arthralgia | 8 | 1 | 5 | 1

*Related to treatment

Gastric Cancer

Combination therapy with DOCETAXEL INJECTION in gastric adenocarcinoma

Data in the following table are based on the experience of 221 patients with advanced gastric adenocarcinoma and no history of prior chemotherapy for advanced disease who were treated with docetaxel 75 mg/m^2 in combination with cisplatin and fluorouracil (see Table 10).
Table 10 - Clinically Important Treatment-Emergent Adverse Reactions Regardless of Relationship to Treatment in the Gastric Cancer Study

 | Docetaxel 75 mg/m^2 + cisplatin 75 mg/m^2 + fluorouracil 750 mg/m^2 n=221 |  | Cisplatin 100 mg/m^2 + fluorouracil 1,000 mg/m^2 n=224
Adverse Reaction | Any % | Grade 3/4 % | Any % | Grade 3/4 %
Anemia | 97 | 18 | 93 | 26
Neutropenia | 96 | 82 | 83 | 57
Fever in the absence of infection | 36 | 2 | 23 | 1
Thrombocytopenia | 26 | 8 | 39 | 14
Infection | 29 | 16 | 23 | 10
Febrile neutropenia | 16 | N/A | 5 | N/A
Neutropenic infection | 16 | N/A | 10 | N/A
Allergic reactions | 10 | 2 | 6 | 0
Fluid retention* | 15 | 0 | 4 | 0
Edema* | 13 | 0 | 3 | 0
Lethargy | 63 | 21 | 58 | 18
Neurosensory | 38 | 8 | 25 | 3
Neuromotor | 9 | 3 | 8 | 3
Dizziness | 16 | 5 | 8 | 2
Alopecia | 67 | 5 | 41 | 1
Rash/itch | 12 | 1 | 9 | 0
Nail changes | 8 | 0 | 0 | 0
Skin desquamation | 2 | 0 | 0 | 0
Nausea | 73 | 16 | 76 | 19
Vomiting | 67 | 15 | 73 | 19
Anorexia | 51 | 13 | 54 | 12
Stomatitis | 59 | 21 | 61 | 27
Diarrhea | 78 | 20 | 50 | 8
Constipation | 25 | 2 | 34 | 3
Esophagitis/dysphagia/ odynophagia | 16 | 2 | 14 | 5
Gastrointestinal pain/cramping | 11 | 2 | 7 | 3
Cardiac dysrhythmias | 5 | 2 | 2 | 1
Myocardial ischemia | 1 | 0 | 3 | 2
Tearing | 8 | 0 | 2 | 0
Altered hearing | 6 | 0 | 13 | 2

Clinically important treatment-emergent adverse reactions were determined based upon frequency, severity, and clinical impact of the adverse reaction.
*Related to treatment

Head and Neck Cancer

Combination therapy with DOCETAXEL INJECTION in head and neck cancer

Table 11 summarizes the safety data obtained from patients that received induction chemotherapy with docetaxel 75 mg/m^2 in combination with cisplatin and fluorouracil followed by radiotherapy (TAX323; 174 patients) or chemoradiotherapy (TAX324; 251 patients). The treatment regimens are described in Section 14.6.
Table 11 – Clinically Important Treatment-Emergent Adverse Reactions (Regardless of Relationship) in Patients with SCCHN Receiving Induction Chemotherapy with Docetaxel in Combination with Cisplatin and Fluorouracil Followed by Radiotherapy (TAX323) or Chemoradiotherapy (TAX324)

 | TAX323 (n=355) |  |  |  | TAX324 (n=494)
 | Docetaxel arm (n=174) |  | Comparator arm (n=181) |  | Docetaxel arm (n=251) |  | Comparator arm (n=243)
Adverse Reaction (by Body System) | Any % | Grade 3/4 % | Any % | Grade 3/4 % | Any % | Grade 3/4 % | Any % | Grade 3/4 %
Neutropenia | 93 | 76 | 87 | 53 | 95 | 84 | 84 | 56
Anemia | 89 | 9 | 88 | 14 | 90 | 12 | 86 | 10
Thrombocytopenia | 24 | 5 | 47 | 18 | 28 | 4 | 31 | 11
Infection | 27 | 9 | 26 | 8 | 23 | 6 | 28 | 5
Febrile neutropenia* | 5 | N/A | 2 | N/A | 12 | N/A | 7 | N/A
Neutropenic infection | 14 | N/A | 8 | N/A | 12 | N/A | 8 | N/A
Cancer pain | 21 | 5 | 16 | 3 | 17 | 9 | 20 | 11
Lethargy | 41 | 3 | 38 | 3 | 61 | 5 | 56 | 10
Fever in the absence of infection | 32 | 1 | 37 | 0 | 30 | 4 | 28 | 3
Myalgia | 10 | 1 | 7 | 0 | 7 | 0 | 7 | 2
Weight loss | 21 | 1 | 27 | 1 | 14 | 2 | 14 | 2
Allergy | 6 | 0 | 3 | 0 | 2 | 0 | 0 | 0
Fluid retention** Edema only Weight gain only | 20 13 6 | 0 0 0 | 14 7 6 | 1 0 0 | 13 12 0 | 1 1 0 | 7 6 1 | 2 1 0
Dizziness | 2 | 0 | 5 | 1 | 16 | 4 | 15 | 2
Neurosensory | 18 | 1 | 11 | 1 | 14 | 1 | 14 | 0
Altered hearing | 6 | 0 | 10 | 3 | 13 | 1 | 19 | 3
Neuromotor | 2 | 1 | 4 | 1 | 9 | 0 | 10 | 2
Alopecia | 81 | 11 | 43 | 0 | 68 | 4 | 44 | 1
Rash/itch | 12 | 0 | 6 | 0 | 20 | 0 | 16 | 1
Dry skin | 6 | 0 | 2 | 0 | 5 | 0 | 3 | 0
Desquamation | 4 | 1 | 6 | 0 | 2 | 0 | 5 | 0
Nausea | 47 | 1 | 51 | 7 | 77 | 14 | 80 | 14
Stomatitis | 43 | 4 | 47 | 11 | 66 | 21 | 68 | 27
Vomiting | 26 | 1 | 39 | 5 | 56 | 8 | 63 | 10
Diarrhea | 33 | 3 | 24 | 4 | 48 | 7 | 40 | 3
Constipation | 17 | 1 | 16 | 1 | 27 | 1 | 38 | 1
Anorexia | 16 | 1 | 25 | 3 | 40 | 12 | 34 | 12
Esophagitis/dysphagia/ Odynophagia | 13 | 1 | 18 | 3 | 25 | 13 | 26 | 10
Taste, sense of smell altered | 10 | 0 | 5 | 0 | 20 | 0 | 17 | 1
Gastrointestinal pain/cramping | 8 | 1 | 9 | 1 | 15 | 5 | 10 | 2
Heartburn | 6 | 0 | 6 | 0 | 13 | 2 | 13 | 1
Gastrointestinal bleeding | 4 | 2 | 0 | 0 | 5 | 1 | 2 | 1
Cardiac dysrhythmia | 2 | 2 | 2 | 1 | 6 | 3 | 5 | 3
Venous*** | 3 | 2 | 6 | 2 | 4 | 2 | 5 | 4
Ischemia myocardial | 2 | 2 | 1 | 0 | 2 | 1 | 1 | 1
Tearing | 2 | 0 | 1 | 0 | 2 | 0 | 2 | 0
Conjunctivitis | 1 | 0 | 1 | 0 | 1 | 0 | 0.4 | 0

Clinically important treatment-emergent adverse reactions based upon frequency, severity, and clinical impact.
*Febrile neutropenia: grade ≥2 fever concomitant with grade 4 neutropenia requiring intravenous antibiotics and/or hospitalization.
**Related to treatment.
*** Includes superficial and deep vein thrombosis and pulmonary embolism

6.2 Postmarketing Experience

The following adverse reactions have been identified from clinical trials and/or postmarketing surveillance. Because these reactions are reported from a population of uncertain size, it is not always possible to reliably estimate their frequency or establish a causal relationship to drug exposure.

Body as a whole: diffuse pain, chest pain, radiation recall phenomenon, injection site recall reaction (recurrence of skin reaction at a site of previous extravasation following administration of docetaxel at a different site) at the site of previous extravasation.

Cardiovascular: atrial fibrillation, deep vein thrombosis, ECG abnormalities, thrombophlebitis, pulmonary embolism, syncope, tachycardia, myocardial infarction. Ventricular arrhythmia, including ventricular tachycardia, in patients treated with docetaxel in combination regimens including doxorubicin, 5-fluorouracil and/or cyclophosphamide, may be associated with fatal outcome.

Cutaneous: cutaneous lupus erythematosus, bullous eruptions such as erythema multiforme and severe cutaneous adverse reactions (SCARs) such as Stevens-Johnson syndrome, toxic epidermal necrolysis and acute generalized exanthematous pustulosis, scleroderma-like changes (usually preceded by peripheral lymphedema), severe palmar-plantar erythrodysesthesia and permanent alopecia.

Gastrointestinal: enterocolitis, including colitis, ischemic colitis, and neutropenic enterocolitis, which may be fatal. Abdominal pain, anorexia, constipation, duodenal ulcer, esophagitis, gastrointestinal hemorrhage, gastrointestinal perforation, intestinal obstruction, ileus, and dehydration as a consequence of gastrointestinal events.

Hearing: ototoxicity, hearing disorders and/or hearing loss, including during use with other ototoxic drugs.

Hematologic: bleeding episodes, disseminated intravascular coagulation (DIC), often in association with sepsis or multiorgan failure.

Hepatic: hepatitis, sometimes fatal, primarily in patients with preexisting liver disorders.

Hypersensitivity: anaphylactic shock with fatal outcome in patients who received premedication. Severe hypersensitivity reactions with fatal outcome with docetaxel in patients who previously experienced hypersensitivity reactions to paclitaxel.

Metabolism and nutrition disorders: electrolyte imbalance, including hyponatremia, hypokalemia, hypomagnesemia, and hypocalcemia. Tumor lysis syndrome, sometimes fatal.

Neurologic: confusion, seizures or transient loss of consciousness, sometimes appearing during the infusion of the drug.

Ophthalmologic: conjunctivitis, lacrimation or lacrimation with or without conjunctivitis, cystoid macular edema (CME). Excessive tearing which may be attributable to lacrimal duct obstruction. Transient visual disturbances (flashes, flashing lights, scotomata), typically occurring during drug infusion and reversible upon discontinuation of the infusion, in association with hypersensitivity reactions.

Respiratory: dyspnea, acute pulmonary edema, acute respiratory distress syndrome/pneumonitis, interstitial lung disease, interstitial pneumonia, respiratory failure, and pulmonary fibrosis, which may be fatal. Radiation pneumonitis in patients receiving concomitant radiotherapy.

Renal: renal insufficiency and renal failure, the majority of cases were associated with concomitant nephrotoxic drugs.

Second primary malignancies: second primary malignancies, including AML, MDS, NHL, and renal cancer [see Warnings and Precautions (5.7)].

Musculoskeletal disorder: myositis.

7 DRUG INTERACTIONS

Docetaxel is a CYP3A4 substrate. In vitro studies have shown that the metabolism of docetaxel may be modified by the concomitant administration of compounds that induce, inhibit, or are metabolized by cytochrome P450 3A4.

In vivo studies showed that the exposure of docetaxel increased 2.2-fold when it was coadministered with ketoconazole, a potent inhibitor of CYP3A4. Protease inhibitors, particularly ritonavir, may increase the exposure of docetaxel. Concomitant use of DOCETAXEL INJECTION and drugs that inhibit CYP3A4 may increase exposure to docetaxel and should be avoided. In patients receiving treatment with DOCETAXEL INJECTION, close monitoring for toxicity and a DOCETAXEL INJECTION dose reduction could be considered if systemic administration of a potent CYP3A4 inhibitor cannot be avoided [see Dosage and Administration (2.7), Clinical Pharmacology (12.3)].

8 USE IN SPECIFIC POPULATIONS

8.1 Pregnancy

Risk Summary
Based on findings in animal reproduction studies and its mechanism of action, DOCETAXEL INJECTION can cause fetal harm when administered to a pregnant woman [see Clinical Pharmacology (12.1)]. Available data from case reports in the literature and pharmacovigilance with docetaxel use in pregnant women are not sufficient to inform the drug-associated risk of major birth defects, miscarriage, or adverse maternal or fetal outcomes. DOCETAXEL INJECTION contains alcohol which can interfere with neurobehavioral development [see Clinical Considerations]. In animal reproductive studies, administration of docetaxel to pregnant rats and rabbits during the period of organogenesis caused an increased incidence of embryo-fetal toxicities, including intrauterine mortality, at doses as low as 0.02 and 0.003 times the recommended human dose based on body surface area, respectively [see Data]. Advise pregnant women and females of reproductive potential of the potential risk to a fetus.
The estimated background risk of major birth defects and miscarriage for the indicated populations is unknown. All pregnancies have a background risk of birth defect, miscarriage, or other adverse outcomes. In the U.S. general population, the estimated background risk of major birth defects and miscarriage in clinically recognized pregnancies is 2% to 4% and 15% to 20%, respectively.
Clinical Considerations
DOCETAXEL INJECTION contains alcohol [see Warnings and Precautions (5.13)]. Published studies have demonstrated that alcohol is associated with fetal harm including central nervous system abnormalities, behavioral disorders, and impaired intellectual development.
Data
Animal data
Intravenous administration of ≥0.3 and 0.03 mg/kg/day docetaxel to pregnant rats and rabbits, respectively, during the period of organogenesis caused an increased incidence of intrauterine mortality, resorptions, reduced fetal weights, and fetal ossification delays. Maternal toxicity was also observed at these doses, which were approximately 0.02 and 0.003 times the daily maximum recommended human dose based on body surface area, respectively.

8.2 Lactation

Risk Summary
There is no information regarding the presence of docetaxel in human milk, or on its effects on milk production or the breastfed child. No lactation studies in animals have been conducted. Because of the potential for serious adverse reactions in a breastfed child, advise women not to breastfeed during treatment with DOCETAXEL INJECTION and for 1 week after the last dose.

8.3 Females and Males of Reproductive Potential

Pregnancy Testing
Verify pregnancy status in females of reproductive potential prior to initiating DOCETAXEL INJECTION.
Contraception
Females
DOCETAXEL INJECTION can cause fetal harm when administered to a pregnant woman [see Use in Specific Populations (8.1)]. Advise females of reproductive potential to use effective contraception during treatment and for 6 months after the last dose of DOCETAXEL INJECTION.
Males
Based on genetic toxicity findings, advise male patients with female partners of reproductive potential to use effective contraception during treatment and for 3 months after the last dose of DOCETAXEL INJECTION.
Infertility
Based on findings in animal studies, DOCETAXEL INJECTION may impair fertility in males of reproductive potential [see Nonclinical Toxicology (13.1)].

8.4 Pediatric Use

The alcohol content of DOCETAXEL INJECTION should be taken into account when given to pediatric patients [see Warnings and Precautions (5.13)].

The efficacy of docetaxel in pediatric patients as monotherapy or in combination has not been established. The overall safety profile of docetaxel in pediatric patients receiving monotherapy or TCF was consistent with the known safety profile in adults.

Another formulation of docetaxel has been studied in a total of 289 pediatric patients: 239 in 2 trials with monotherapy and 50 in combination treatment with cisplatin and 5-fluoruracil (TCF).

Docetaxel Monotherapy

Docetaxel monotherapy was evaluated in a dose-finding phase 1 trial in 61 pediatric patients (median age 12.5 years, range 1-22 years) with a variety of refractory solid tumors. The recommended dose was 125 mg/m^2 as a 1-hour intravenous infusion every 21 days. The primary dose limiting toxicity was neutropenia.

The recommended dose for docetaxel monotherapy was evaluated in a phase 2 single-arm trial in 178 pediatric patients (median age 12 years, range 1-26 years) with a variety of recurrent/refractory solid tumors. Efficacy was not established with tumor response rates ranging from one complete response (CR) (0.6%) in a patient with undifferentiated sarcoma to four partial responses (2.2%) seen in one patient each with Ewing Sarcoma, neuroblastoma, osteosarcoma, and squamous cell carcinoma.

Docetaxel in Combination

Docetaxel was studied in combination with cisplatin and 5-fluorouracil (TCF) versus cisplatin and 5-fluorouracil (CF) for the induction treatment of nasopharyngeal carcinoma (NPC) in pediatric patients prior to chemoradiation consolidation. Seventy-five patients (median age 16 years, range 9 to 21 years) were randomized (2:1) to docetaxel (75 mg/m^2) in combination with cisplatin (75 mg/m^2) and 5-fluorouracil (750 mg/m²) (TCF) or to cisplatin (80 mg/m^2) and 5-fluorouracil (1,000 mg/m^2/day) (CF). The primary endpoint was the CR rate following induction treatment of NPC. One patient out of 50 in the TCF group (2%) had a complete response while none of the 25 patients in the CF group had a complete response.

Pharmacokinetics

Pharmacokinetic parameters for docetaxel were determined in 2 pediatric solid tumor trials. Following docetaxel administration at 55 mg/m^2 to 235 mg/m^2 in a 1-hour intravenous infusion every 3 weeks in 25 patients aged 1 to 20 years (median 11 years), docetaxel clearance was 17.3±10.9 L/h/m^2.

Docetaxel was administered in combination with cisplatin and 5-fluorouracil (TCF), at dose levels of 75 mg/m^2 in a 1-hour intravenous infusion day 1 in 28 patients aged 10 to 21 years (median 16 years, 17 patients were older than 16). Docetaxel clearance was 17.9±8.75 L/h/m^2, corresponding to an AUC of 4.20±2.57 μg.h/mL.

In summary, the body surface area adjusted clearance of docetaxel monotherapy and TCF combination in children were comparable to those in adults [see Clinical Pharmacology (12.3)].

8.5 Geriatric Use

In general, dose selection for an elderly patient should be cautious, reflecting the greater frequency of decreased hepatic, renal, or cardiac function and of concomitant disease or other drug therapy in elderly patients.

Non-small Cell Lung Cancer

In a study conducted in chemotherapy-naive patients with NSCLC (TAX326), 148 patients (36%) in the docetaxel+cisplatin group were 65 years of age or greater. There were 128 patients (32%) in the vinorelbine+cisplatin group 65 years of age or greater. In the docetaxel+cisplatin group, patients less than 65 years of age had a median survival of 10.3 months (95% CI: 9.1 months, 11.8 months) and patients 65 years or older had a median survival of 12.1 months (95% CI: 9.3 months, 14 months). In patients 65 years of age or greater treated with docetaxel+cisplatin, diarrhea (55%), peripheral edema (39%) and stomatitis (28%) were observed more frequently than in the vinorelbine+cisplatin group (diarrhea 24%, peripheral edema 20%, stomatitis 20%). Patients treated with docetaxel+cisplatin who were 65 years of age or greater were more likely to experience diarrhea (55%), infections (42%), peripheral edema (39%) and stomatitis (28%) compared to patients less than the age of 65 administered the same treatment (43%, 31%, 31% and 21%, respectively).

When docetaxel was combined with carboplatin for the treatment of chemotherapy-naive, advanced non-small cell lung carcinoma, patients 65 years of age or greater (28%) experienced higher frequency of infection compared to similar patients treated with docetaxel+cisplatin, and a higher frequency of diarrhea, infection and peripheral edema than elderly patients treated with vinorelbine+cisplatin.

Prostate Cancer

Of the 333 patients treated with docetaxel every three weeks plus prednisone in the prostate cancer study (TAX327), 209 patients were 65 years of age or greater and 68 patients were older than 75 years. In patients treated with docetaxel every three weeks, the following treatment-emergent adverse reactions occurred at rates ≥10% higher in patients 65 years of age or greater compared to younger patients: anemia (71% vs 59%), infection (37% vs 24%), nail changes (34% vs 23%), anorexia (21% vs 10%), weight loss (15% vs 5%), respectively.

Breast Cancer

In the adjuvant breast cancer trial (TAX316), docetaxel in combination with doxorubicin and cyclophosphamide was administered to 744 patients of whom 48 (6%) were 65 years of age or greater. The number of elderly patients who received this regimen was not sufficient to determine whether there were differences in safety and efficacy between elderly and younger patients.

Gastric Cancer

Among the 221 patients treated with docetaxel in combination with cisplatin and fluorouracil in the gastric cancer study, 54 were 65 years of age or older and 2 patients were older than 75 years. In this study, the number of patients who were 65 years of age or older was insufficient to determine whether they respond differently from younger patients. However, the incidence of serious adverse reactions was higher in the elderly patients compared to younger patients. The incidence of the following adverse reactions (all grades, regardless of relationship): lethargy, stomatitis, diarrhea, dizziness, edema, febrile neutropenia/neutropenic infection occurred at rates ≥10% higher in patients who were 65 years of age or older compared to younger patients. Elderly patients treated with TCF should be closely monitored.

Head and Neck Cancer

Among the 174 and 251 patients who received the induction treatment with docetaxel in combination with cisplatin and fluorouracil (TPF) for SCCHN in the TAX323 and TAX324 studies, 18 (10%) and 32 (13%) of the patients were 65 years of age or older, respectively.

These clinical studies of docetaxel in combination with cisplatin and fluorouracil in patients with SCCHN did not include sufficient numbers of patients aged 65 and over to determine whether they respond differently from younger patients. Other reported clinical experience with this treatment regimen has not identified differences in responses between elderly and younger patients.

8.6 Hepatic Impairment

Avoid DOCETAXEL INJECTION in patients with bilirubin > ULN and patients with AST and/or ALT > 1.5 x ULN concomitant with alkaline phosphatase > 2.5 x ULN [see Boxed Warning, Warnings and Precautions (5.2), Clinical Pharmacology (12.3)].

The alcohol content of DOCETAXEL INJECTION should be taken into account when given to patients with hepatic impairment [see Warnings and Precautions (5.13)].

10 OVERDOSAGE

There is no known antidote for DOCETAXEL INJECTION overdosage. In case of overdosage, the patient should be kept in a specialized unit where vital functions can be closely monitored. Anticipated complications of overdosage include: bone marrow suppression, peripheral neurotoxicity, and mucositis. Patients should receive therapeutic G-CSF as soon as possible after discovery of overdose. Other appropriate symptomatic measures should be taken, as needed.

In two reports of overdose, one patient received 150 mg/m^2 and the other received 200 mg/m^2 as 1-hour infusions. Both patients experienced severe neutropenia, mild asthenia, cutaneous reactions, and mild paresthesia, and recovered without incident.

In mice, lethality was observed following single intravenous doses that were ≥154 mg/kg (about 4.5 times the human dose of 100 mg/m^2 on a mg/m^2 basis); neurotoxicity associated with paralysis, non-extension of hind limbs, and myelin degeneration was observed in mice at 48 mg/kg (about 1.5 times the human dose of 100 mg/m^2 basis). In male and female rats, lethality was observed at a dose of 20 mg/kg (comparable to the human dose of 100 mg/m^2 on a mg/m^2 basis) and was associated with abnormal mitosis and necrosis of multiple organs.

11 DESCRIPTION

Docetaxel is an antineoplastic agent belonging to the taxoid family. It is prepared by semisynthesis beginning with a precursor extracted from the renewable needle biomass of yew plants. The chemical name for docetaxel (anhydrous) is (2R,3S)-N-carboxy-3-phenylisoserine,N-tert-butyl ester, 13-ester with 5β-20-epoxy-1,2α,4,7β,10β,13α-hexahydroxytax-11-en-9-one 4-acetate 2-benzoate. Docetaxel (anhydrous) has the following structural formula:

Docetaxel anhydrous, USP is a white to almost-white powder with molecular formula of C43H53NO14, and a molecular weight of 807.88. It is highly lipophilic and practically insoluble in water.
One-vial DOCETAXEL INJECTION

DOCETAXEL INJECTION USP is a sterile, non-pyrogenic, yellowish colour solution at 20 mg/mL concentration.

Each mL contains 20 mg docetaxel (anhydrous) and 4 mg citric acid anhydrous in 0.54 grams polysorbate 80 and 0.395 grams dehydrated alcohol (50% v/v) solution.

DOCETAXEL INJECTION USP is available in single-dose vials containing 20 mg (1 mL), 80 mg (4 mL), or 160 mg (8 mL) docetaxel (anhydrous).

DOCETAXEL INJECTION USP requires NO prior dilution with a diluent and is ready to add to the infusion solution.

12 CLINICAL PHARMACOLOGY

12.1 Mechanism of Action

Docetaxel is an antineoplastic agent that acts by disrupting the microtubular network in cells that is essential for mitotic and interphase cellular functions. Docetaxel binds to free tubulin and promotes the assembly of tubulin into stable microtubules while simultaneously inhibiting their disassembly. This leads to the production of microtubule bundles without normal function and to the stabilization of microtubules, which results in the inhibition of mitosis in cells. Docetaxel’s binding to microtubules does not alter the number of protofilaments in the bound microtubules, a feature which differs from most spindle poisons currently in clinical use.

12.3 Pharmacokinetics

Absorption

The pharmacokinetics of docetaxel has been evaluated in cancer patients after administration of 20 mg/m^2 to 115 mg/m^2 in phase 1 studies. The area under the curve (AUC) was dose proportional following doses of 70 mg/m^2 to 115 mg/m^2 with infusion times of 1 to 2 hours. Docetaxel’s pharmacokinetic profile is consistent with a three-compartment pharmacokinetic model, with half-lives for the α, β, and γ phases of 4 min, 36 min, and 11.1 hour, respectively. Mean total body clearance was 21 L/h/m^2.
Distribution

The initial rapid decline represents distribution to the peripheral compartments and the late (terminal) phase is due, in part, to a relatively slow efflux of docetaxel from the peripheral compartment. Mean steady state volume of distribution was 113 L. In vitro studies showed that docetaxel is about 94% protein bound, mainly to α1-acid glycoprotein, albumin, and lipoproteins. In three cancer patients, the in vitro binding to plasma proteins was found to be approximately 97%. Dexamethasone does not affect the protein binding of docetaxel.
Metabolism

In vitro drug interaction studies revealed that docetaxel is metabolized by the CYP3A4 isoenzyme, and its metabolism may be modified by the concomitant administration of compounds that induce, inhibit, or are metabolized by cytochrome P450 3A4 [see Drug Interactions (7)].
Elimination

A study of ^14C-docetaxel was conducted in three cancer patients. Docetaxel was eliminated in both the urine and feces following oxidative metabolism of the tert-butyl ester group, but fecal excretion was the main elimination route. Within 7 days, urinary and fecal excretion accounted for approximately 6% and 75% of the administered radioactivity, respectively. About 80% of the radioactivity recovered in feces is excreted during the first 48 hours as 1 major and 3 minor metabolites with very small amounts (less than 8%) of unchanged drug.
Specific Populations

Effect of Age: A population pharmacokinetic analysis was carried out after docetaxel treatment of 535 patients dosed at 100 mg/m^2. Pharmacokinetic parameters estimated by this analysis were very close to those estimated from phase 1 studies. The pharmacokinetics of docetaxel was not influenced by age. Effect of Gender: The population pharmacokinetics analysis described above also indicated that gender did not influence the pharmacokinetics of docetaxel.
Hepatic Impairment: The population pharmacokinetic analysis described above indicated that in patients with clinical chemistry data suggestive of mild to moderate liver impairment (AST and/or ALT >1.5 times ULN concomitant with alkaline phosphatase > 2.5 times ULN), total body clearance was lowered by an average of 27%, resulting in a 38% increase in systemic exposure (AUC). This average, however, includes a substantial range and there is, at present, no measurement that would allow recommendation for dose adjustment in such patients. Patients with combined abnormalities of transaminase and alkaline phosphatase should not be treated with DOCETAXEL INJECTION. Patients with severe hepatic impairment have not been studied [see Warnings and Precautions (5.2), Use in Specific Populations (8.6)].
Effect of Race: Mean total body clearance for Japanese patients dosed at the range of 10 mg/m^2 to 90 mg/m^2 was similar to that of European/American populations dosed at 100 mg/m^2, suggesting no significant difference in the elimination of docetaxel in the two populations.
Drug Interaction Studies

Effect of Ketoconazole: The effect of ketoconazole (a strong CYP3A4 inhibitor) on the pharmacokinetics of docetaxel was investigated in 7 cancer patients. Patients were randomized to receive either docetaxel (100 mg/m^2 intravenous) alone or docetaxel (10 mg/m^2 intravenous) in combination with ketoconazole (200 mg orally once daily for 3 days) in a crossover design with a 3-week washout period. The results of this study indicated that the mean dose-normalized AUC of docetaxel was increased 2.2-fold and its clearance was reduced by 49% when docetaxel was coadministered with ketoconazole [see Dosage and Administration (2.7), Drug Interactions (7)].
Effect of combination therapies

- Dexamethasone: Docetaxel total body clearance was not modified by pretreatment with dexamethasone.
- Cisplatin: Clearance of docetaxel in combination therapy with cisplatin was similar to that previously observed following monotherapy with docetaxel. The pharmacokinetic profile of cisplatin in combination therapy with docetaxel was similar to that observed with cisplatin alone.
- Cisplatin and Fluorouracil: The combined administration of docetaxel, cisplatin and fluorouracil in 12 patients with solid tumors had no influence on the pharmacokinetics of each individual drug.
- Prednisone: A population pharmacokinetic analysis of plasma data from 40 patients with metastatic castration-resistant prostate cancer indicated that docetaxel systemic clearance in combination with prednisone is similar to that observed following administration of docetaxel alone.
- Cyclophosphamide and Doxorubicin: A study was conducted in 30 patients with advanced breast cancer to determine the potential for drug-drug interactions between docetaxel (75 mg/m2), doxorubicin (50 mg/m2), and cyclophosphamide (500 mg/m2) when administered in combination. The coadministration of docetaxel had no effect on the pharmacokinetics of doxorubicin and cyclophosphamide when the three drugs were given in combination compared to coadministration of doxorubicin and cyclophosphamide only. In addition, doxorubicin and cyclophosphamide had no effect on docetaxel plasma clearance when the three drugs were given in combination compared to historical data for docetaxel monotherapy.

13 NONCLINICAL TOXICOLOGY

13.1 Carcinogenesis, Mutagenesis, Impairment of Fertility

Carcinogenicity studies with docetaxel have not been performed.
Docetaxel was clastogenic in the in vitro chromosome aberration test in CHO-K1 cells and in the in vivo micronucleus test in mice administered doses of 0.39 to 1.56 mg/kg (about 1/60th to 1/15th the recommended human dose on a mg/m^2 basis). Docetaxel was not mutagenic in the Ames test or the CHO/HGPRT gene mutation assays.
Docetaxel did not reduce fertility in rats when administered in multiple intravenous doses of up to 0.3 mg/kg (about 1/50th the recommended human dose on a mg/m^2 basis), but decreased testicular weights were reported. This correlates with findings of a 10-cycle toxicity study (dosing once every 21 days for 6 months) in rats and dogs in which testicular atrophy or degeneration was observed at intravenous doses of 5 mg/kg in rats and 0.375 mg/kg in dogs (about 1/3rd and 1/15th the recommended human dose on a mg/m^2 basis, respectively). An increased frequency of dosing in rats produced similar effects at lower dose levels.

14 CLINICAL STUDIES

14.1 Locally Advanced or Metastatic Breast Cancer

The efficacy and safety of docetaxel have been evaluated in locally advanced or metastatic breast cancer after failure of previous chemotherapy (alkylating agent-containing regimens or anthracycline-containing regimens).

Randomized Trials

In one randomized trial, patients with a history of prior treatment with an anthracycline-containing regimen were assigned to treatment with docetaxel (100 mg/m^2 every 3 weeks) or the combination of mitomycin (12 mg/m^2 every 6 weeks) and vinblastine (6 mg/m^2 every 3 weeks). Two hundred three patients were randomized to docetaxel and 189 to the comparator arm. Most patients had received prior chemotherapy for metastatic disease; only 27 patients on the docetaxel arm and 33 patients on the comparator arm entered the study following relapse after adjuvant therapy. Three-quarters of patients had measurable, visceral metastases. The primary endpoint was time to progression. The following table summarizes the study results (See Table 12).

Table 12 - Efficacy of Docetaxel in the Treatment of Breast Cancer Patients Previously Treated with an Anthracycline-Containing Regimen (Intent-to-Treat Analysis)

Efficacy Parameter | Docetaxel (n=203) | Mitomycin/ Vinblastine (n=189) | p-value
Median Survival | 11.4 months | 8.7 months | p=0.01 Log Rank
Risk Ratio*, Mortality (Docetaxel: Control) 95% CI (Risk Ratio) | 0.73 0.58-0.93 |  | p=0.01 Log Rank
Median Time to Progression | 4.3 months | 2.5 months | p=0.01 Log Rank
Risk Ratio*, Progression (Docetaxel: Control) 95% CI (Risk Ratio) | 0.75 0.61-0.94 |  | p=0.01 Log Rank
Overall Response Rate Complete Response Rate | 28.1% 3.4% | 9.5% 1.6% | p<0.0001 Chi Square

*For the risk ratio, a value less than 1.00 favors docetaxel.

In a second randomized trial, patients previously treated with an alkylating-containing regimen were assigned to treatment with docetaxel (100 mg/m^2) or doxorubicin (75 mg/m^2) every 3 weeks. One hundred sixty-one patients were randomized to docetaxel and 165 patients to doxorubicin. Approximately one-half of patients had received prior chemotherapy for metastatic disease, and one-half entered the study following relapse after adjuvant therapy. Three-quarters of patients had measurable, visceral metastases. The primary endpoint was time to progression. The study results are summarized below (See Table 13).

Table 13 - Efficacy of Docetaxel in the Treatment of Breast Cancer Patients Previously Treated with an Alkylating-Containing Regimen (Intent-to-Treat Analysis)

Efficacy Parameter | Docetaxel (n=161) | Doxorubicin (n=165) | p-value
Median Survival | 14.7 months | 14.3 months | p=0.39 Log Rank
Risk Ratio*, Mortality (Docetaxel: Control) 95% CI (Risk Ratio) | 0.89 0.68-1.16 |  | p=0.39 Log Rank
Median Time to Progression | 6.5 months | 5.3 months | p=0.45 Log Rank
Risk Ratio*, Progression (Docetaxel: Control) 95% CI (Risk Ratio) | 0.93 0.71-1.16 |  | p=0.45 Log Rank
Overall Response Rate Complete Response Rate | 45.3% 6.8% | 29.7% 4.2% | p=0.004 Chi Square

*For the risk ratio, a value less than 1 favors docetaxel.

In another multicenter open-label, randomized trial (TAX313), in the treatment of patients with advanced breast cancer who progressed or relapsed after one prior chemotherapy regimen, 527 patients were randomized to receive docetaxel monotherapy 60 mg/m^2 (n=151), 75 mg/m^2 (n=188) or 100 mg/m^2 (n=188). In this trial, 94% of patients had metastatic disease and 79% had received prior anthracycline therapy. Response rate was the primary endpoint. Response rates increased with docetaxel dose: 19.9% for the 60 mg/m^2 group compared to 22.3% for the 75 mg/m^2 and 29.8% for the 100 mg/m^2 group; pair-wise comparison between the 60 mg/m^2 and 100 mg/m^2 groups was statistically significant (p=0.037).

Single Arm Studies

Docetaxel at a dose of 100 mg/m^2 was studied in six single arm studies involving a total of 309 patients with metastatic breast cancer in whom previous chemotherapy had failed. Among these, 190 patients had anthracycline-resistant breast cancer, defined as progression during an anthracycline-containing chemotherapy regimen for metastatic disease, or relapse during an anthracycline-containing adjuvant regimen. In anthracycline-resistant patients, the overall response rate was 37.9% (72/190; 95% CI: 31.0% to 44.8%) and the complete response rate was 2.1%.

Docetaxel was also studied in three single arm Japanese studies at a dose of 60 mg/m^2, in 174 patients who had received prior chemotherapy for locally advanced or metastatic breast cancer. Among 26 patients whose best response to an anthracycline had been progression, the response rate was 34.6% (95% CI: 17.2% to 55.7%), similar to the response rate in single arm studies of 100 mg/m^2.

14.2 Adjuvant Treatment of Breast Cancer

A multicenter, open-label, randomized trial (TAX316) evaluated the efficacy and safety of docetaxel for the adjuvant treatment of patients with axillary-node-positive breast cancer and no evidence of distant metastatic disease. After stratification according to the number of positive lymph nodes (1 to 3, 4+), 1,491 patients were randomized to receive either docetaxel 75 mg/m^2 administered 1-hour after doxorubicin 50 mg/m^2 and cyclophosphamide 500 mg/m^2 (TAC arm), or doxorubicin 50 mg/m^2 followed by fluorouracil 500 mg/m^2 and cyclophosphamide 500 mg/m^2 (FAC arm). Both regimens were administered every 3 weeks for 6 cycles. Docetaxel was administered as a 1-hour infusion; all other drugs were given as intravenous bolus on day 1. In both arms, after the last cycle of chemotherapy, patients with positive estrogen and/or progesterone receptors received tamoxifen 20 mg daily for up to 5 years. Adjuvant radiation therapy was prescribed according to guidelines in place at participating institutions and was given to 69% of patients who received TAC and 72% of patients who received FAC.

Results from a second interim analysis (median follow-up 55 months) are as follows: In study TAX316, the docetaxel-containing combination regimen TAC showed significantly longer disease-free survival (DFS) than FAC (hazard ratio=0.74; 2-sided 95% CI=0.6, 0.92, stratified log rank p=0.0047). The primary endpoint, disease-free survival, included local and distant recurrences, contralateral breast cancer and deaths from any cause. The overall reduction in risk of relapse was 25.7% for TAC-treated patients. (See Figure 1).

At the time of this interim analysis, based on 219 deaths, overall survival was longer for TAC than FAC (hazard ratio=0.69, 2-sided 95% CI=0.53, 0.9). (See Figure 2). There will be further analysis at the time survival data mature.
Figure 1: TAX316 Disease Free Survival K-M curve

Figure 2: TAX316 Overall Survival K-M Curve

The following table describes the results of subgroup analyses for DFS and OS (See Table 14).
Table 14 - Subset Analyses-Adjuvant Breast Cancer Study

 |  | Disease Free Survival |  | Overall Survival
Patient subset | Number of patients | Hazard ratio* | 95% CI | Hazard ratio* | 95% CI
No. of positive nodes Overall 1 to 3 4+ | 744 467 277 | 0.74 0.64 0.84 | (0.6, 0.92) (0.47, 0.87) (0.63, 1.12) | 0.69 0.45 0.93 | (0.53, 0.9) (0.29, 0.7) (0.66, 1.32)
Receptor status Positive Negative | 566 178 | 0.76 0.68 | (0.59, 0.98) (0.48, 0.97) | 0.69 0.66 | (0.48, 0.99) (0.44, 0.98)

*a hazard ratio of less than 1 indicates that TAC is associated with a longer disease free survival or overall survival compared to FAC.

14.3 Non-small Cell Lung Cancer (NSCLC)

The efficacy and safety of docetaxel has been evaluated in patients with unresectable, locally advanced or metastatic non-small cell lung cancer whose disease has failed prior platinum-based chemotherapy or in patients who are chemotherapy naive.

Monotherapy with Docetaxel for NSCLC Previously Treated with Platinum-Based Chemotherapy

Two randomized, controlled trials established that a docetaxel dose of 75 mg/m^2 was tolerable and yielded a favorable outcome in patients previously treated with platinum-based chemotherapy (see below). Docetaxel at a dose of 100 mg/m^2, however, was associated with unacceptable hematologic toxicity, infections, and treatment-related mortality and this dose should not be used [see Boxed Warning, Dosage and Administration (2.7), Warnings and Precautions (5.3)].

One trial (TAX317), randomized patients with locally advanced or metastatic non-small cell lung cancer, a history of prior platinum-based chemotherapy, no history of taxane exposure, and an ECOG performance status ≤ 2 to docetaxel or best supportive care. The primary endpoint of the study was survival. Patients were initially randomized to docetaxel 100 mg/m^2 or best supportive care, but early toxic deaths at this dose led to a dose reduction to docetaxel 75 mg/m^2. A total of 104 patients were randomized in this amended study to either docetaxel 75 mg/m^2 or best supportive care.

In a second randomized trial (TAX320), 373 patients with locally advanced or metastatic non-small cell lung cancer, a history of prior platinum-based chemotherapy, and an ECOG performance status ≤ 2 were randomized to docetaxel 75 mg/m^2, docetaxel 100 mg/m^2 and a treatment in which the investigator chose either vinorelbine 30 mg/m^2 days 1, 8, and 15 repeated every 3 weeks or ifosfamide 2 g/m^2 days 1-3 repeated every 3 weeks. Forty percent of the patients in this study had a history of prior paclitaxel exposure. The primary endpoint was survival in both trials. The efficacy data for the docetaxel 75 mg/m^2 arm and the comparator arms are summarized in Table 15 and Figures 3 and 4 showing the survival curves for the two studies.
Table 15 - Efficacy of Docetaxel in the Treatment of Non-small Cell Lung Cancer Patients Previously Treated with a Platinum-Based Chemotherapy Regimen (Intent-to-Treat Analysis)

 | TAX317 |  | TAX320
 | Docetaxel 75 mg/m^2 n=55 | Best Supportive Care n=49 | Docetaxel 75 mg/m^2 n=125 | Control (V/I*) n=123
Overall Survival Log-rank Test | p=0.01 |  | p=0.13
Risk Ratio††, Mortality (Docetaxel: Control) 95% CI (Risk Ratio) | 0.56 (0.35, 0.88) |  | 0.82 (0.63, 1.06)
Median Survival 95% CI | 7.5 months** (5.5, 12.8) | 4.6 months (3.7, 6.1) | 5.7 months (5.1, 7.1) | 5.6 months (4.4, 7.9)
% 1-year Survival 95% CI | 37%**† (24, 50) | 12% (2, 23) | 30%**† (22, 39) | 20% (13, 27)
Time to Progression 95% CI | 12.3 weeks** (9.0, 18.3) | 7 weeks (6.0, 9.3) | 8.3 weeks (7.0, 11.7) | 7.6 weeks (6.7, 10.1)
Response Rate 95% CI | 5.5% (1.1, 15.1) | Not Applicable | 5.7% (2.3, 11.3) | 0.8% (0, 4.5)

* Vinorelbine/Ifosfamide
**p≤0.05
† uncorrected for multiple comparisons
†† a value less than 1 favors docetaxel.

Only one of the two trials (TAX317) showed a clear effect on survival, the primary endpoint; that trial also showed an increased rate of survival to one year. In the second study (TAX320) the rate of survival at one year favored docetaxel 75 mg/m^2.

Figure 3 - TAX317 Survival K-M Curves - Docetaxel 75 mg/m^2 Versus Best Supportive Care
Figure 4 - TAX320 Survival K-M Curves – Docetaxel 75 mg/m^2 Versus Vinorelbine or Ifosfamide Control

Patients treated with docetaxel at a dose of 75 mg/m^2 experienced no deterioration in performance status and body weight relative to the comparator arms used in these trials.

Combination Therapy with Docetaxel for Chemotherapy-Naive NSCLC

In a randomized controlled trial (TAX326), 1218 patients with unresectable stage IIIB or IV NSCLC and no prior chemotherapy were randomized to receive one of three treatments: docetaxel 75 mg/m^2 as a 1 hour infusion immediately followed by cisplatin 75 mg/m^2 over 30 to 60 minutes every 3 weeks; vinorelbine 25 mg/m^2 administered over 6-10 minutes on days 1, 8, 15, 22 followed by cisplatin 100 mg/m^2 administered on day 1 of cycles repeated every 4 weeks; or a combination of docetaxel and carboplatin.

The primary efficacy endpoint was overall survival. Treatment with docetaxel+cisplatin did not result in a statistically significantly superior survival compared to vinorelbine+cisplatin (see table below). The 95% confidence interval of the hazard ratio (adjusted for interim analysis and multiple comparisons) shows that the addition of docetaxel to cisplatin results in an outcome ranging from a 6% inferior to a 26% superior survival compared to the addition of vinorelbine to cisplatin. The results of a further statistical analysis showed that at least (the lower bound of the 95% confidence interval) 62% of the known survival effect of vinorelbine when added to cisplatin (about a 2-month increase in median survival; Wozniak et al. JCO, 1998) was maintained. The efficacy data for the docetaxel+cisplatin arm and the comparator arm are summarized in Table 16.

Table 16 - Survival Analysis of Docetaxel in Combination Therapy for Chemotherapy-Naive NSCLC

Comparison | Docetaxel+Cisplatin n=408 | Vinorelbine+Cisplatin n=405
Kaplan-Meier Estimate of Median Survival | 10.9 months | 10 months
p-valuea | 0.122
Estimated Hazard Ratiob | 0.88
Adjusted 95% CIc | (0.74, 1.06)

a From the superiority test (stratified log rank) comparing docetaxel+cisplatin to vinorelbine+cisplatin
bHazard ratio of docetaxel+cisplatin vs. vinorelbine+cisplatin. A hazard ratio of less than 1 indicates that docetaxel+cisplatin is associated with a longer survival.
cAdjusted for interim analysis and multiple comparisons.

The second comparison in the same three-arm study, vinorelbine+cisplatin versus docetaxel+carboplatin, did not demonstrate superior survival associated with the docetaxel arm (Kaplan-Meier estimate of median survival was 9.1 months for docetaxel+carboplatin compared to 10.0 months on the vinorelbine+cisplatin arm) and the docetaxel+carboplatin arm did not demonstrate preservation of at least 50% of the survival effect of vinorelbine added to cisplatin. Secondary endpoints evaluated in the trial included objective response and time to progression. There was no statistically significant difference between docetaxel+cisplatin and vinorelbine+cisplatin with respect to objective response and time to progression (see Table 17).

Table 17 - Response and TTP Analysis of Docetaxel in Combination Therapy for Chemotherapy-Naive NSCLC

Endpoint | Docetaxel+Cisplatin | Vinorelbine+Cisplatin | p-value
Objective Response Rate (95% CI)a | 31.6% (26.5%, 36.8%) | 24.4% (19.8%, 29.2%) | Not Significant
Median Time to Progressionb (95% CI)a | 21.4 weeks (19.3, 24.6) | 22.1 weeks (18.1, 25.6) | Not Significant

aAdjusted for multiple comparisons.
bKaplan-Meier estimates.

14.4 Castration-Resistant Prostate Cancer

The safety and efficacy of docetaxel in combination with prednisone in patients with metastatic castration-resistant prostate cancer were evaluated in a randomized multicenter active control trial. A total of 1006 patients with Karnofsky Performance Status (KPS) ≥60 were randomized to the following treatment groups:

- Docetaxel 75 mg/m^2 every 3 weeks for 10 cycles.
- Docetaxel 30 mg/m^2 administered weekly for the first 5 weeks in a 6-week cycle for 5 cycles.
- Mitoxantrone 12 mg/m^2 every 3 weeks for 10 cycles.

All 3 regimens were administered in combination with prednisone 5 mg twice daily, continuously.

In the docetaxel every three week arm, a statistically significant overall survival advantage was demonstrated compared to mitoxantrone. In the docetaxel weekly arm, no overall survival advantage was demonstrated compared to the mitoxantrone control arm. Efficacy results for the docetaxel every 3 week arm versus the control arm are summarized in Table 18 and Figure 5.

Table 18 - Efficacy of Docetaxel in the Treatment of Patients with Metastatic Castration-Resistant Prostate Cancer (Intent-to-Treat Analysis)

 | Docetaxel+Prednisone every 3 weeks | Mitoxantrone+Prednisone every 3 weeks
Number of patients Median survival (months) 95% CI Hazard ratio 95% CI p-value* | 335 18.9 (17.0-21.2) 0.761 (0.619-0.936) 0.0094 | 337 16.5 (14.4-18.6) -- -- --

*Stratified log-rank test. Threshold for statistical significance = 0.0175 because of 3 arms.

Figure 5 - TAX327 Survival K-M Curves

14.5 Gastric Adenocarcinoma

A multicenter, open-label, randomized trial was conducted to evaluate the safety and efficacy of docetaxel for the treatment of patients with advanced gastric adenocarcinoma, including adenocarcinoma of the gastroesophageal junction, who had not received prior chemotherapy for advanced disease. A total of 445 patients with KPS >70 were treated with either docetaxel (T) (75 mg/m^2 on day 1) in combination with cisplatin (C) (75 mg/m^2 on day 1) and fluorouracil (F) (750 mg/m^2 per day for 5 days) or cisplatin (100 mg/m^2 on day 1) and fluorouracil (1,000 mg/m^2 per day for 5 days). The length of a treatment cycle was 3 weeks for the TCF arm and 4 weeks for the CF arm. The demographic characteristics were balanced between the two treatment arms. The median age was 55 years, 71% were male, 71% were Caucasian, 24% were 65 years of age or older, 19% had a prior curative surgery and 12% had palliative surgery. The median number of cycles administered per patient was 6 (with a range of 1 to 16) for the TCF arm compared to 4 (with a range of 1 to 12) for the CF arm. Time to progression (TTP) was the primary endpoint and was defined as time from randomization to disease progression or death from any cause within 12 weeks of the last evaluable tumor assessment or within 12 weeks of the first infusion of study drugs for patients with no evaluable tumor assessment after randomization. The hazard ratio (HR) for TTP was 1.47 (CF/TCF, 95% CI: 1.19 to 1.83) with a significantly longer TTP (p=0.0004) in the TCF arm. Approximately 75% of patients had died at the time of this analysis. Overall survival was significantly longer (p=0.0201) in the TCF arm with a HR of 1.29 (95% CI: 1.04-1.61). Efficacy results are summarized in Table 19 and Figures 6 and 7.

Table 19 - Efficacy of Docetaxel (T) in the Treatment of Patients with Gastric Adenocarcinoma

Endpoint | TCF n=221 | CF n=224
Median TTP (months) (95% CI) Hazard ratio† (95% CI) *p-value | 5.6 (4.86 to 5.91) | 3.7 (3.45 to 4.47)
Median TTP (months) (95% CI) Hazard ratio† (95% CI) *p-value | 0.68 (0.55 to 0.84) 0.0004
Median survival (months) (95% CI) Hazard ratio† (95% CI) *p-value | 9.2 (8.38 to 10.58) | 8.6 (7.16 to 9.46)
Median survival (months) (95% CI) Hazard ratio† (95% CI) *p-value | 0.77 (0.62 to 0.96) 0.0201
Overall Response Rate (CR+PR) (%) | 36.7 | 25.4
p-value | 0.0106

*Unstratified log-rank test
†For the hazard ratio (TCF/CF), values less than 1 favor the docetaxel arm.

Subgroup analyses were consistent with the overall results across age, gender and race.

Figure 6 - Gastric Cancer Study (TAX325) Time to Progression K-M Curve
Figure 7 -Gastric Cancer Study (TAX325) Survival K-M Curve

14.6 Head and Neck Cancer

Induction Chemotherapy Followed by Radiotherapy (TAX323)

The safety and efficacy of docetaxel in the induction treatment of patients with squamous cell carcinoma of the head and neck (SCCHN) was evaluated in a multicenter, open-label, randomized trial (TAX323). In this study, 358 patients with inoperable locally advanced SCCHN, and WHO performance status 0 or 1, were randomized to one of two treatment arms. Patients on the docetaxel arm received docetaxel (T) 75 mg/m^2 followed by cisplatin (P) 75 mg/m^2 on Day 1, followed by fluorouracil (F) 750 mg/m^2 per day as a continuous infusion on Days 1 to 5. The cycles were repeated every three weeks for 4 cycles. Patients whose disease did not progress received radiotherapy (RT) according to institutional guidelines (TPF/RT). Patients on the comparator arm received cisplatin (P) 100 mg/m^2 on Day 1, followed by fluorouracil (F) 1,000 mg/m^2/day as a continuous infusion on Days 1 to 5. The cycles were repeated every three weeks for 4 cycles. Patients whose disease did not progress received RT according to institutional guidelines (PF/RT). At the end of chemotherapy, with a minimal interval of 4 weeks and a maximal interval of 7 weeks, patients whose disease did not progress received radiotherapy (RT) according to institutional guidelines. Locoregional therapy with radiation was delivered either with a conventional fraction regimen (1.8 Gy to 2.0 Gy once a day, 5 days per week for a total dose of 66 to 70 Gy) or with an accelerated/hyperfractionated regimen (twice a day, with a minimum interfraction interval of 6 hours, 5 days per week, for a total dose of 70 to 74 Gy, respectively). Surgical resection was allowed following chemotherapy, before or after radiotherapy.

The primary endpoint in this study, progression-free survival (PFS), was significantly longer in the TPF arm compared to the PF arm, p=0.0077 (median PFS: 11.4 vs 8.3 months, respectively) with an overall median follow- up time of 33.7 months. Median overall survival with a median follow-up of 51.2 months was also significantly longer in favor of the TPF arm compared to the PF arm (median OS: 18.6 vs 14.2 months,respectively). Efficacy results are presented in Table 20 and Figures 8 and 9.

Table 20 - Efficacy of Docetaxel in the Induction Treatment of Patients with Inoperable Locally Advanced SCCHN (Intent-to-Treat Analysis)

Endpoint | Docetaxel + Cisplatin+ Fluorouracil n=177 | Cisplatin+ Fluorouracil n=181
Median progression free survival (months) (95% CI) Adjusted Hazard ratio (95% CI) *p-value | 11.4 (10.1 to 14) | 8.3 (7.4 to 9.1)
Median progression free survival (months) (95% CI) Adjusted Hazard ratio (95% CI) *p-value | 0.71 (0.56 to 0.91) 0.0077
Median survival (months) (95% CI) Hazard ratio (95% CI) **p-value | 18.6 (15.7 to 24) | 14.2 (11.5 to 18.7)
Median survival (months) (95% CI) Hazard ratio (95% CI) **p-value | 0.71 (0.56 to 0.9) 0.0055
Best overall response (CR + PR) to chemotherapy (%) (95% CI) ***p-value | 67.8 (60.4 to 74.6) | 53.6 (46 to 61)
Best overall response (CR + PR) to chemotherapy (%) (95% CI) ***p-value | 0.006
Best overall response (CR + PR) to study treatment [chemotherapy +/-radiotherapy] (%) (95% CI) ***p-value | 72.3 (65.1 to 78.8) | 58.6 (51 to 65.8)
Best overall response (CR + PR) to study treatment [chemotherapy +/-radiotherapy] (%) (95% CI) ***p-value | 0.006

A Hazard ratio of less than 1 favors Docetaxel+Cisplatin+Fluorouracil
* Stratified log-rank test based on primary tumor site
** Stratified log-rank test, not adjusted for multiple comparisons
*** Chi square test, not adjusted for multiple comparisons
Figure 8 -TAX323 Progression-Free Survival K-M Curve

Figure 9 -TAX323 Overall Survival K-M Curve

Induction Chemotherapy Followed by Chemoradiotherapy (TAX324)

The safety and efficacy of docetaxel in the induction treatment of patients with locally advanced (unresectable, low surgical cure, or organ preservation) SCCHN was evaluated in a randomized, multicenter open-label trial (TAX324). In this study, 501 patients, with locally advanced SCCHN, and a WHO performance status of 0 or 1, were randomized to one of two treatment arms. Patients on the docetaxel arm received docetaxel (T) 75 mg/m² by intravenous infusion on day 1 followed by cisplatin (P) 100 mg/m² administered as a 30-minute to three-hour intravenous infusion, followed by the continuous intravenous infusion of fluorouracil (F) 1,000 mg/m²/day from day 1 to day 4. The cycles were repeated every 3 weeks for 3 cycles. Patients on the comparator arm received cisplatin (P) 100 mg/m² as a 30-minute to three-hour intravenous infusion on day 1 followed by the continuous intravenous infusion of fluorouracil (F) 1,000 mg/m²/day from day 1 to day 5. The cycles were repeated every 3 weeks for 3 cycles.

All patients in both treatment arms who did not have progressive disease were to receive 7 weeks of chemoradiotherapy (CRT) following induction chemotherapy 3 to 8 weeks after the start of the last cycle. During radiotherapy, carboplatin (AUC 1.5) was given weekly as a one-hour intravenous infusion for a maximum of 7 doses. Radiation was delivered with megavoltage equipment using once daily fractionation (2 Gy per day, 5 days per week for 7 weeks for a total dose of 70-72 Gy). Surgery on the primary site of disease and/or neck could be considered at anytime following completion of CRT. The primary efficacy endpoint, overall survival (OS), was significantly longer (log-rank test, p=0.0058) with the docetaxel-containing regimen compared to PF [median OS: 70.6 vs 30.1 months, respectively, hazard ratio (HR)=0.7, 95% confidence interval (CI)= 0.54 – 0.9]. Overall survival results are presented in Table 21 and Figure 10.

Table 21 - Efficacy of Docetaxel in the Induction Treatment of Patients with Locally Advanced SCCHN (Intent-to-Treat Analysis)

Endpoint | Docetaxel + Cisplatin + Fluorouracil n=255 | Cisplatin + Fluorouracil n=246
Median overall survival (months) (95% CI) | 70.6 (49 to NE) | 30.1 (20.9 to 51.5)
Hazard ratio: (95% CI) *p-value | 0.7 (0.54 to 0.9) 0.0058

A Hazard ratio of less than 1 favors docetaxel+cisplatin+fluorouracil
* un-adjusted log-rank test
NE - not estimable

Figure 10: TAX324 Overall Survival K-M Curve

15 REFERENCES

1. “OSHA Hazardous Drugs.” http://www.osha.gov/SLTC/hazardousdrugs/index.html

16 HOW SUPPLIED/STORAGE AND HANDLING

16.1 How Supplied

DOCETAXEL INJECTION is supplied in a single-dose vial for 20 mg/mL, single-dose vial for 80 mg/4 mL and single-dose vial for 160 mg/8 mL as a sterile, pyrogen-free, non-aqueous solution. Discard unused portion.

DOCETAXEL INJECTION 20 mg/mL: NDC 47335-323-40

The vial is in a blister pack in one carton.

DOCETAXEL INJECTION 80 mg/4 mL: NDC 47335-895-40

The vial is in a blister pack in one carton.

DOCETAXEL INJECTION 160 mg/8 mL: NDC 47335-939-40

The vial is in a blister pack in one carton.

16.2 Storage

Store at 20° to 25°C (68° to 77°F); excursions permitted between 15° and 30°C (59° and 86°F) [see USP Controlled Room Temperature]. Retain in the original package to protect from light.

16.3 Handling and Disposal

DOCETAXEL INJECTION is a cytotoxic drug. Follow applicable special handling and disposal procedures.^1

17 PATIENT COUNSELING INFORMATION

Advise the patient to read the FDA-approved patient labeling (Patient Information).

Bone Marrow Suppression

Advise patients that periodic assessment of their blood count will be performed to detect neutropenia, thrombocytopenia, and/ or anemia [see Contraindications (4), Warnings and Precautions (5.3)]. Instruct patients to monitor their temperature frequently and immediately report any occurrence of fever.

Enterocolitis and Neutropenic Colitis

Advise patients of the symptoms of colitis, such as abdominal pain or tenderness, and/or diarrhea, with or without fever, and instruct patients to promptly contact their healthcare provider if they experience these symptoms [see Dosage and Administration (2.7) and Warnings and Precautions (5.4)].

Hypersensitivity Reactions

Ask patients whether they have previously received paclitaxel therapy, and if they have experienced a hypersensitivity reaction to paclitaxel. Instruct patients to immediately report to their healthcare provider signs of a hypersensitivity reaction. [see Contraindications (4), Warnings and Precautions (5.5)].

Fluid Retention

Advise patients to report signs of fluid retention such as peripheral edema in the lower extremities, weight gain, and dyspnea immediately to their healthcare provider [see Warnings and Precautions (5.6)].

Second Primary Malignancies

Advise patients on the risk of second primary malignancies during treatment with DOCETAXEL INJECTION [see Warnings and Precautions (5.7)].

Cutaneous Reactions

Advise patients that localized erythema of the extremities and severe skin toxicities may occur. Instruct patients to immediately report severe cutaneous reactions to their healthcare provider [see Dosage and Administration (2.7) and Warnings and Precautions (5.8)].

Neurologic Reactions

Advise patients that neurosensory symptoms or peripheral neuropathy may occur. Instruct patients to immediately report neurologic reactions to their healthcare provider [see Dosage and Administration (2.7) and Warnings and Precautions (5.9)].

Eye Disorders

Advise patients that vision disturbances and excessive tearing are associated with DOCETAXEL INJECTION administration. Instruct patients to immediately report any vision changes to their healthcare provider [see Warnings and Precautions (5.10)].

Gastrointestinal Reactions

Explain to patients that nausea, vomiting, diarrhea, and constipation are associated with DOCETAXEL INJECTION administration. Instruct patients to report any severe events to their healthcare provider [see Adverse Reactions (6)].

Cardiac Disorders

Advise patients to report any irregular and/or rapid heartbeat, severe shortness of breath, dizziness, and/or fainting immediately to their healthcare provider [see Adverse Reactions (6)].

Other Common Adverse Reactions

Advise patients that other common adverse reactions associated with DOCETAXEL INJECTION may include alopecia (cases of permanent hair loss have been reported), asthenia, anorexia, dysgeusia, mucositis, myalgia, nail disorders, or pain. Instruct patients to report these reactions to their healthcare provider if serious events occur [see Adverse Reactions (6)].

Importance of Corticosteroids

Explain the significance of oral corticosteroids such as dexamethasone administration to the patient to help facilitate compliance. Instruct patients to report to their healthcare provider if they were not compliant with the oral corticosteroid regimen [see Dosage and Administration (2.6)].

Embryo-Fetal Toxicity

DOCETAXEL INJECTION can cause fetal harm. Advise patients to inform their healthcare provider of a known or suspected pregnancy. Advise patients to avoid becoming pregnant while receiving this drug. Advise female patients of reproductive potential to use effective contraceptives during treatment and for 6 months after the last dose of DOCETAXEL INJECTION. Advise male patients with female partners of reproductive potential to use effective contraception during treatment and for 3 months after the last dose of DOCETAXEL INJECTION [see Warnings and Precautions (5.12), and Use in Specific Populations (8.1, 8.3)].

Lactation

Advise women not to breastfeed during DOCETAXEL INJECTION treatment and for 1 week after the last dose [see Use in Specific Populations (8.2)].

Infertility

Advise males of reproductive potential that DOCETAXEL INJECTION may impair fertility [see Nonclinical Toxicology (13.1)].

Alcohol Content in DOCETAXEL INJECTION

Explain to patients the possible effects of the alcohol content in DOCETAXEL INJECTION, including possible effects on the central nervous system [see Warnings and Precautions (5.13)].

Tumor Lysis Syndrome

Advise patients of the potential risk of tumor lysis syndrome and to immediately report any signs or symptoms associated with this event (nausea, vomiting, confusion, shortness of breath, seizure, irregular heartbeat, dark or cloudy urine, reduced amount of urine, unusual tiredness, muscle cramps) to their healthcare provider. Advise patients of the importance of keeping scheduled appointment for blood work or other laboratory tests and of drinking adequate fluids to avoid dehydration. [see Warnings and Precautions (5.14)].

Ability to Drive or Operate Machines

Explain to patients that DOCETAXEL INJECTION may impair their ability to drive or operate machines due to its side effects [see Adverse Reactions (6)] or due to the alcohol content of DOCETAXEL INJECTION [see Warnings and Precautions (5.13)]. Advise them not to drive or use machines if they experience these side effects during treatment.

Drug Interactions

Inform patients about the risk of drug interactions and the importance of providing a list of prescription and non-prescription drugs to their healthcare provider [see Drug Interactions (7)].

Patient Information

DOCETAXEL (doe-se-TAKS-el) INJECTION
for intravenous use

What is the most important information I should know about DOCETAXEL INJECTION?
DOCETAXEL INJECTION can cause serious side effects, including death.

- The chance of death in people who receive DOCETAXEL INJECTION is higher if you:
  - have liver problems
  - receive high doses of DOCETAXEL INJECTION
  - have non-small cell lung cancer and have been treated with chemotherapy medicines that contain platinum
- DOCETAXEL INJECTION can affect your blood cells. Your healthcare provider should do routine blood tests during treatment with DOCETAXEL INJECTION. This will include regular checks of your white blood cell counts. If your white blood cells are too low, your healthcare provider may not treat you with DOCETAXEL INJECTION until you have enough white blood cells. People with low white blood cell counts can develop life-threatening infections. The earliest sign of infection may be fever. Follow your healthcare provider’s instructions for how often to take your temperature during treatment with DOCETAXEL INJECTION. Call your healthcare provider right away if you have a fever.
- Swelling (inflammation) of the small intestine and colon. This can happen at any time during treatment and could lead to death as early as the first day you get symptoms. Tell your healthcare provider right away if you develop new or worse symptoms of intestinal problems, including stomach (abdominal) pain or tenderness or diarrhea, with or without fever.
  - Severe allergic reactions are medical emergencies that can happen in people who receive DOCETAXEL INJECTION and can lead to death. You may be at higher risk of developing a severe allergic reaction to DOCETAXEL INJECTION if you are allergic to paclitaxel. Your healthcare provider will monitor you closely for allergic reactions during your DOCETAXEL INJECTION infusion.

Tell your healthcare provider right away if you have any of these signs of a severe allergic reaction:

-
  - trouble breathing
  - sudden swelling of your face, lips, tongue, throat, or trouble swallowing
  - hives (raised bumps), rash, or redness all over your body
- Your body may hold too much fluid (severe fluid retention) during treatment with DOCETAXEL INJECTION. This can be life threatening. To decrease the chance of this happening, you must take another medicine, a corticosteroid, before each DOCETAXEL INJECTION treatment. You must take the corticosteroid exactly as your healthcare provider tells you. Tell your healthcare provider or nurse before your DOCETAXEL INJECTION treatment if you forgot to take your corticosteroid dose or do not take it as your healthcare provider tells you. Tell your healthcare provider right away if you have swelling in your legs or feet, weight gain or shortness of breath.
- Risk of new cancers. An increase in new (second) cancers has happened in people treated with DOCETAXEL INJECTION together with certain other anticancer treatments. This includes certain blood cancers, such as acute myeloid leukemia (AML), myelodysplastic syndrome (MDS), Non-Hodgkin’s Lymphoma (NHL), and kidney cancer.
  - Changes in blood counts due to leukemia and other blood disorders may occur years after treatment with DOCETAXEL INJECTION.

Your healthcare provider will check you for new cancers during and after your treatment with DOCETAXEL INJECTION.

- Severe skin problems.

Tell your healthcare provider right away if you have any of these signs of a severe skin reaction:

- redness and swelling of your arms and legs.
- blistering, peeling or bleeding on any part of your skin (including your lips, eyes, mouth, nose, genitals, hands or feet) with or without a rash. You may also have flu-like symptoms such as fever, chills, or muscle aches.
- red, scaly rash all over your body with blisters small red or white bumps under the skin that contain pus (pustules) and fever.

What is DOCETAXEL INJECTION?
DOCETAXEL INJECTION is a prescription anticancer medicine used to treat certain people with:

- breast cancer
- non-small cell lung cancer
- prostate cancer
- stomach cancer
- head and neck cancer

It is not known if DOCETAXEL INJECTION is effective in children.

Do not receive DOCETAXEL INJECTION if you:

- have a low white blood cell count.
- have had a severe allergic reaction to:
  - docetaxel, the active ingredient in DOCETAXEL INJECTION, or
  - any other medicines that contain polysorbate 80. Ask your healthcare provider or pharmacist if you are not sure.

See “What is the most important information I should know about DOCETAXEL INJECTION?” for the signs and symptoms of a severe allergic reaction.
See the end of this Patient Information for a complete list of the ingredients in DOCETAXEL INJECTION.

Before you receive DOCETAXEL INJECTION, tell your healthcare provider about all of your medical conditions, including if you:

- are allergic to any medicines, including paclitaxel. See “Do not receive DOCETAXEL INJECTION if you”.
- have liver problems
- have kidney problems
- are pregnant or plan to become pregnant. DOCETAXEL INJECTION can harm your unborn baby. You should not become pregnant during treatment with DOCETAXEL INJECTION. Tell your healthcare provider if you become pregnant or you think you may be pregnant during treatment with DOCETAXEL INJECTION.

Females who are able to become pregnant:

- Your healthcare provider will check to see if you are pregnant before you start treatment with DOCETAXEL INJECTION.
- You should use effective birth control (contraception) during treatment with DOCETAXEL INJECTION and for 6 months after the last dose.

Males with female partners who are able to become pregnant should use effective birth control during treatment with DOCETAXEL INJECTION and for 3 months after the last dose.
Talk to your healthcare provider if you have questions about birth control options that are right for you.

- are breastfeeding or plan to breastfeed. It is not known if DOCETAXEL INJECTION passes into your breast milk. Do not breastfeed during treatment with DOCETAXEL INJECTION and for 1 week after the last dose.

Tell your healthcare provider about all the medicines you take, including prescription and over-the-counter medicines, vitamins, and herbal supplements. DOCETAXEL INJECTION may affect the way other medicines work, and other medicines may affect the way DOCETAXEL INJECTION works.
Know the medicines you take. Keep a list of them to show your healthcare provider and pharmacist when you get a new medicine.

How will I receive DOCETAXEL INJECTION?

- DOCETAXEL INJECTION will be given to you as an intravenous (IV) injection into your vein, usually over 1 hour.
- DOCETAXEL INJECTION is usually given every 3 weeks.
- Your healthcare provider will decide how long you will receive treatment with DOCETAXEL INJECTION.
- Your healthcare provider will check your blood cell counts and other blood tests during your treatment with DOCETAXEL INJECTION to check for side effects of DOCETAXEL INJECTION.

Your healthcare provider may stop your treatment, change the timing of your treatment, or change the dose of your treatment if you have certain side effects while receiving DOCETAXEL INJECTION.

What are the possible side effects of DOCETAXEL INJECTION?
DOCETAXEL INJECTION may cause serious side effects including death.

- See “What is the most important information I should know about DOCETAXEL INJECTION?”
- Neurologic problems. Neurologic symptoms are common in people who receive DOCETAXEL INJECTION but can be severe. Tell your healthcare provider right away if you have numbness, tingling, or burning in your hands or feet (peripheral neuropathy) or weakness of your legs, feet, arms, or hands (motor weakness).
- Vision problems including blurred vision or loss of vision. Tell your healthcare provider right away if you have any vision changes.
- DOCETAXEL INJECTION contains alcohol. The alcohol content in DOCETAXEL INJECTION may impair your ability to drive or use machinery right after receiving DOCETAXEL INJECTION. Consider whether you should drive, operate machinery or do other dangerous activities right after you receive DOCETAXEL INJECTION treatment.
- Tumor lysis syndrome (TLS). TLS is caused by the fast breakdown of cancer cells. TLS can cause kidney failure, the need for dialysis treatment, or heart problems, and may lead to death. Your healthcare provider will do blood tests to check for TLS when you first start treatment and during treatment with DOCETAXEL INJECTION. Tell your healthcare provider right away if you have any symptoms of TLS during treatment with DOCETAXEL INJECTION, including:
  - nausea
  - confusion
  - vomitting
  - Shortness of breath
  - irregular heartbeat
  - dark or cloudy urine
  - reduced amount of urine
  - unusual tiredness
  - muscle cramps
- You may experience side effects of DOCETAXEL INJECTION that may impair your ability to drive, use tools, or operate machines. If this happens, do not drive or use any tools or machines before discussing with your healthcare provider.

The most common side effects of DOCETAXEL INJECTION include:

- infections
- low white blood cells (help fight infections), low red blood cells (anemia) and low platelets (help blood to clot)
- allergic reactions (See “What is the most important information I should know about DOCETAXEL INJECTION?”)
- changes in your sense of taste
- shortness of breath
- constipation
- decreased appetite
- changes in your fingernails or toenails
- swelling of your hands, face or feet
- feeling weak or tired
- joint and muscle pain
- nausea and vomiting
- diarrhea
- mouth or lip sores
- hair loss: in some people, permanent hair loss has been reported
- redness of the eye, excess tearing
- skin reactions at the site of DOCETAXEL INJECTION administration such as increased skin pigmentation, redness, tenderness, swelling, warmth or dryness of the skin
- tissue damage if DOCETAXEL INJECTION leaks out of the vein into the tissues

Tell your healthcare provider if you have a fast or irregular heartbeat, severe shortness of breath, dizziness or fainting during your infusion. If any of these events occurs after your infusion, get medical help right away.DOCETAXEL INJECTION may affect fertility in males. Talk to your healthcare provider if this is a concern for you.
These are not all the possible side effects of DOCETAXEL INJECTION. For more information, ask your healthcare provider or pharmacist.
Call your healthcare provider for medical advice about side effects. You may report side effects to FDA at 1-800-FDA-1088.

General information about the safe and effective use of DOCETAXEL INJECTION.
Medicines are sometimes prescribed for purposes other than those listed in this Patient Information. You can ask your pharmacist or healthcare provider for information about DOCETAXEL INJECTION that is written for health professionals.

What are the ingredients in DOCETAXEL INJECTION?
Active ingredient: docetaxel
Inactive ingredients: citric acid anhydrous, polysorbate 80 and dehydrated alcohol solution
Distributed by: Sun Pharmaceutical Industries, Inc. Cranbury, NJ 08512
Manufactured by: Sun Pharmaceutical Ind. Ltd. Halol-Baroda Highway, Halol-389 350, Gujarat, India.
PJPI0669
For more information call 1-800-818-4555.

This Patient Information has been approved by the U.S. Food and Drug Administration.
Revised: 02/2021

Every three-week injection of DOCETAXEL INJECTION for breast, non-small cell lung and stomach, and head and neck cancers.
Take your oral corticosteroid medicine as your healthcare provider tells you.
Oral corticosteroid dosing: Day 1 Date:_________ Time:______AM _______PM
Day 2 Date:_________ Time:______AM _______PM
(DOCETAXEL INJECTION Treatment Day)
Day 3 Date:_________ Time:______AM _______PM

Every three-week injection of DOCETAXEL INJECTION for prostate cancer.
Take your oral corticosteroid medicine as your healthcare provider tells you.
Oral corticosteroid dosing:
Date:___________ Time:___________
Date:___________ Time:___________
(DOCETAXEL INJECTION Treatment Day)
Time:___________

PACKAGE LABEL.PRINCIPAL DISPLAY PANEL-20MG/ML-LABEL

NDC 47335-323-40
Docetaxel Injection, USP
20 mg/mL
Rx only
Cytotoxic Agent
For Intravenous Infusion Only
Ready to add to infusion solution
See Prescribing Information for complete instructions.

PACKAGE LABEL.PRINCIPAL DISPLAY PANEL-80MG/4 ML-LABEL

NDC 47335-895-40
Docetaxel Injection, USP
80 mg/4 mL (20 mg/mL)
Rx only
Cytotoxic Agent
For Intravenous Infusion Only
Ready to add to infusion solution
See Prescribing Information for complete instructions.

PACKAGE LABEL.PRINCIPAL DISPLAY PANEL-20MG/ML-CARTON

NDC 47335-323-40
Docetaxel Injection, USP
20 mg/mL
READY TO ADD TO INFUSION SOLUTION.
For Intravenous Infusion Only
Contains 1 mL
Rx only
SUN PHARMA

PACKAGE LABEL.PRINCIPAL DISPLAY PANEL-80MG/4 ML-CARTON

NDC 47335-895-40
Docetaxel Injection, USP
80 mg/4 mL(20 mg/mL)
READY TO ADD TO INFUSION SOLUTION.
For Intravenous Infusion Only
Contains 4 mL
Rx only
SUN PHARMA

PACKAGE LABEL.PRINCIPAL DISPLAY PANEL-160MG/ 8 ML-LABEL

NDC 47335-939-40
Docetaxel Injection, USP
160 mg/8 mL(20 mg/mL)
Rx only
Cytotoxic Agent
For Intravenous Infusion Only
Ready to add to infusion solution
See Prescribing Information for complete instructions.

PACKAGE LABEL.PRINCIPAL DISPLAY PANEL-160MG/8 ML-CARTON

NDC 47335-939-40
Docetaxel Injection, USP
160 mg/8 mL(20 mg/mL)
READY TO ADD TO INFUSION SOLUTION.
For Intravenous Infusion Only
Contains 8 mL
Rx only
SUN PHARMA